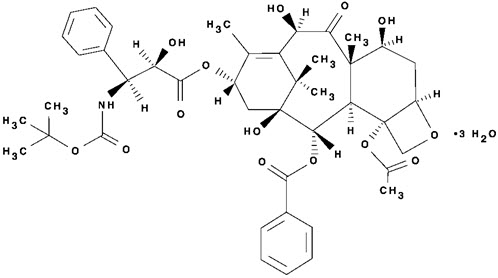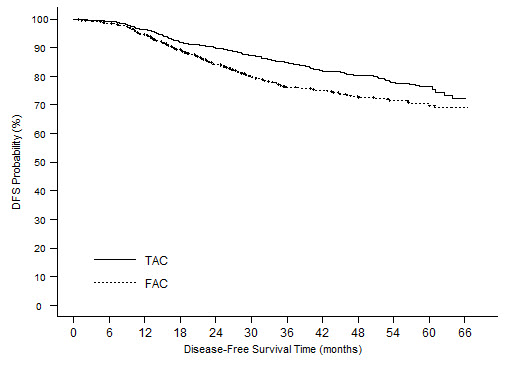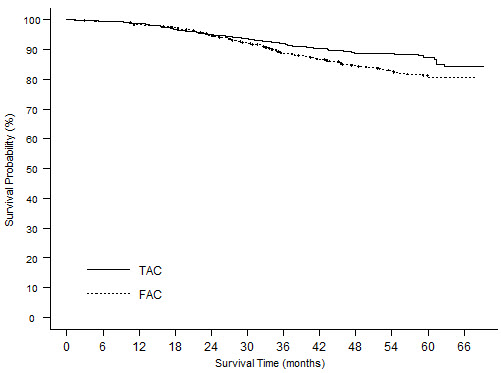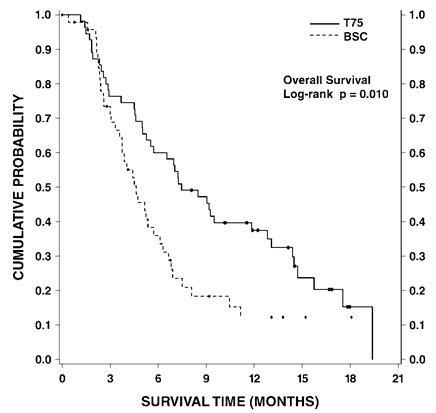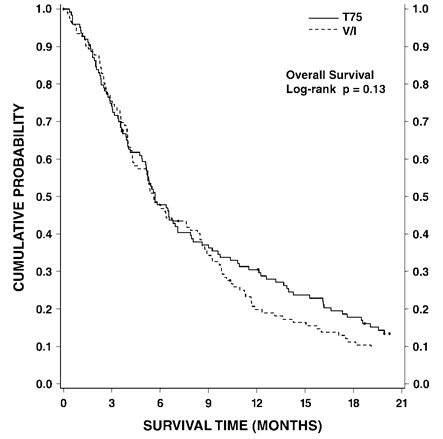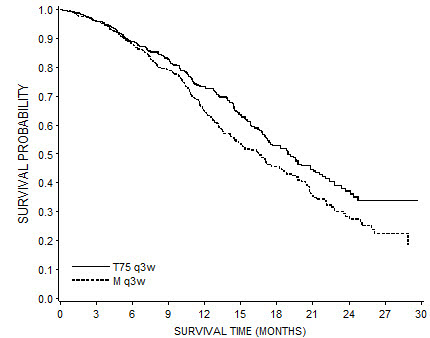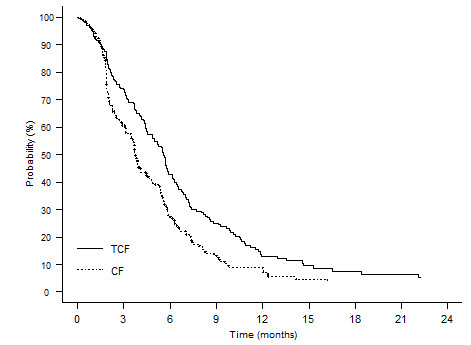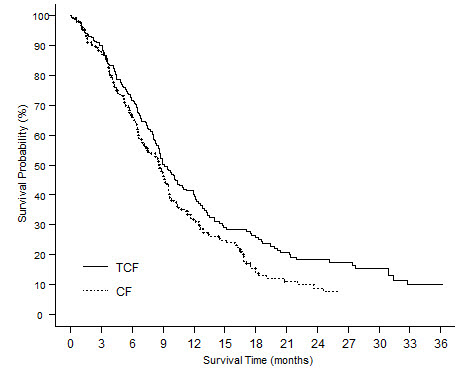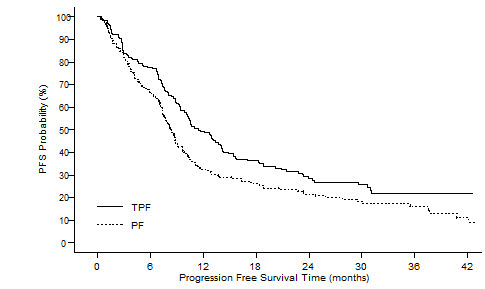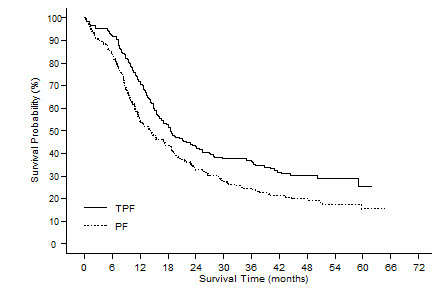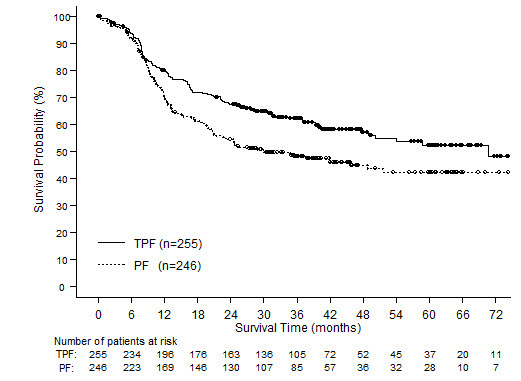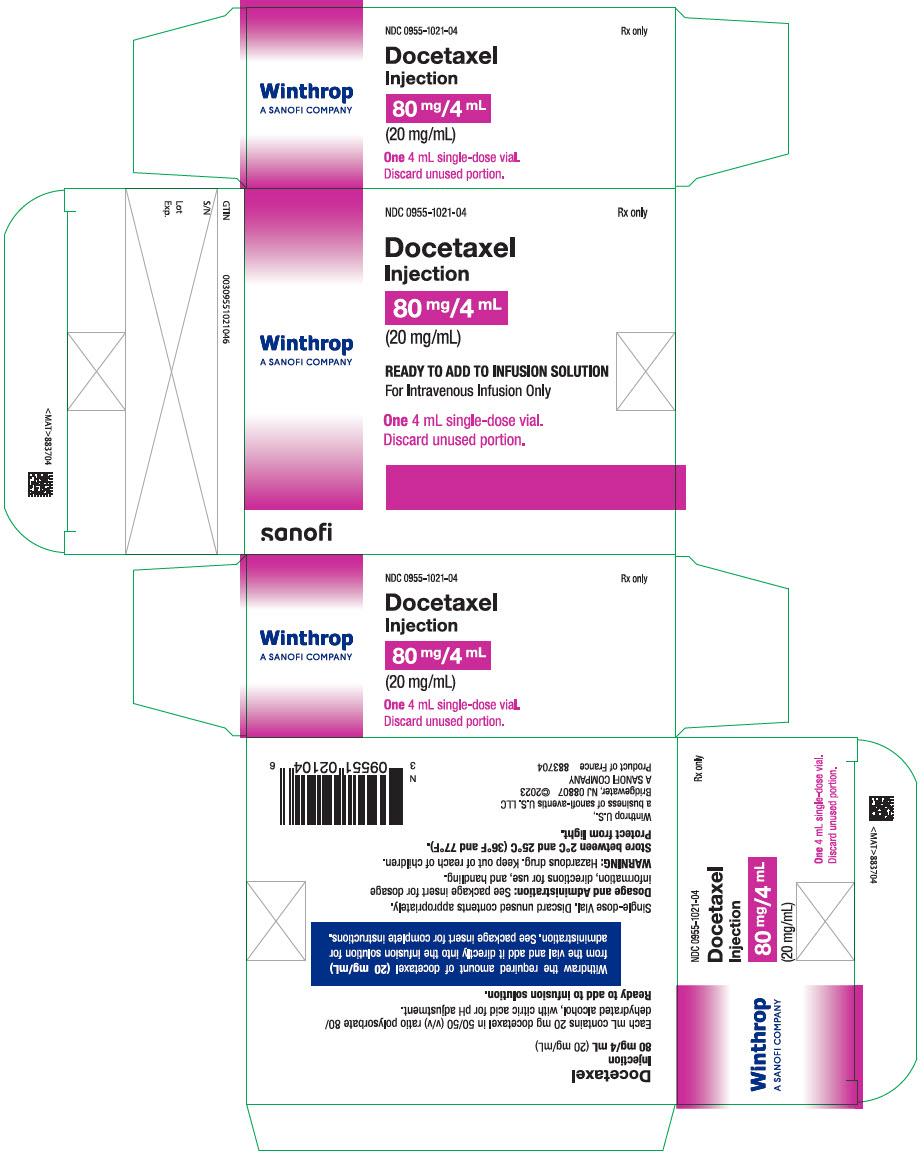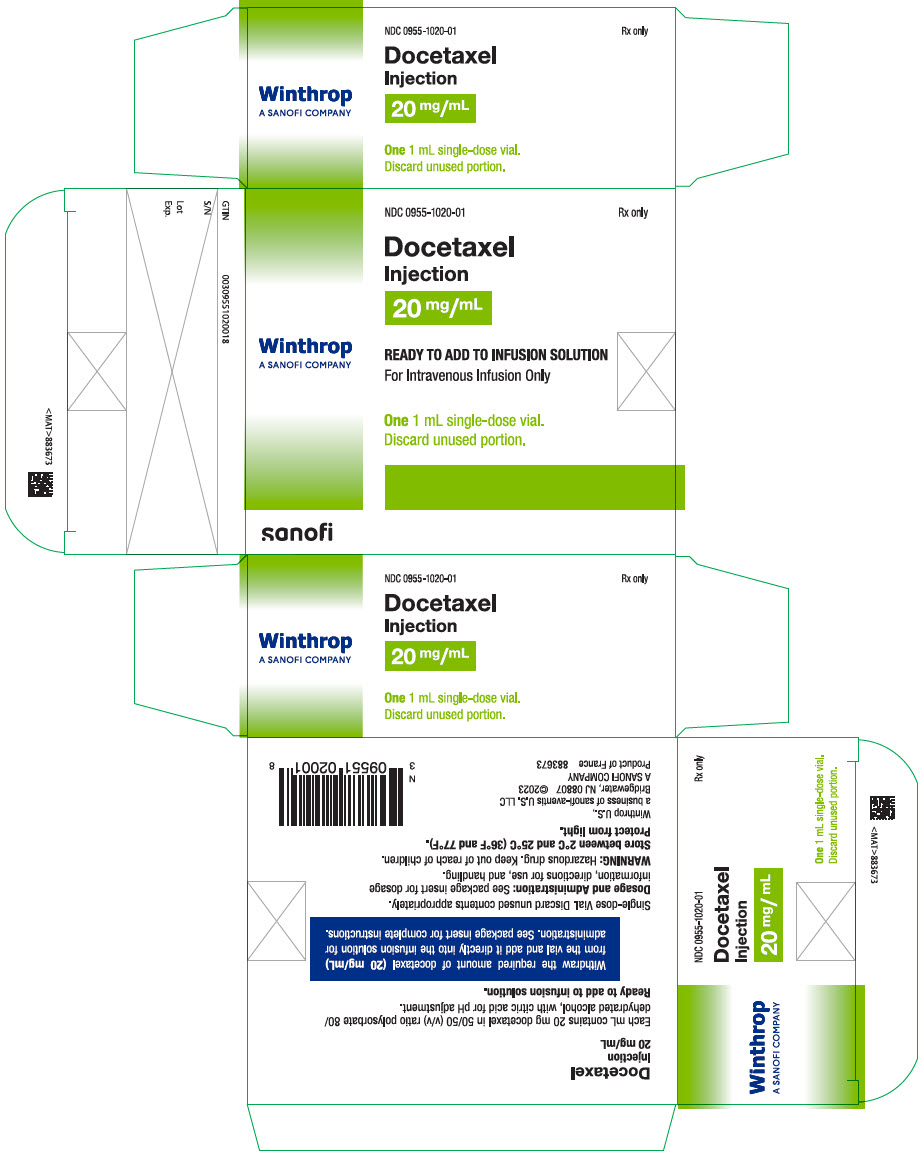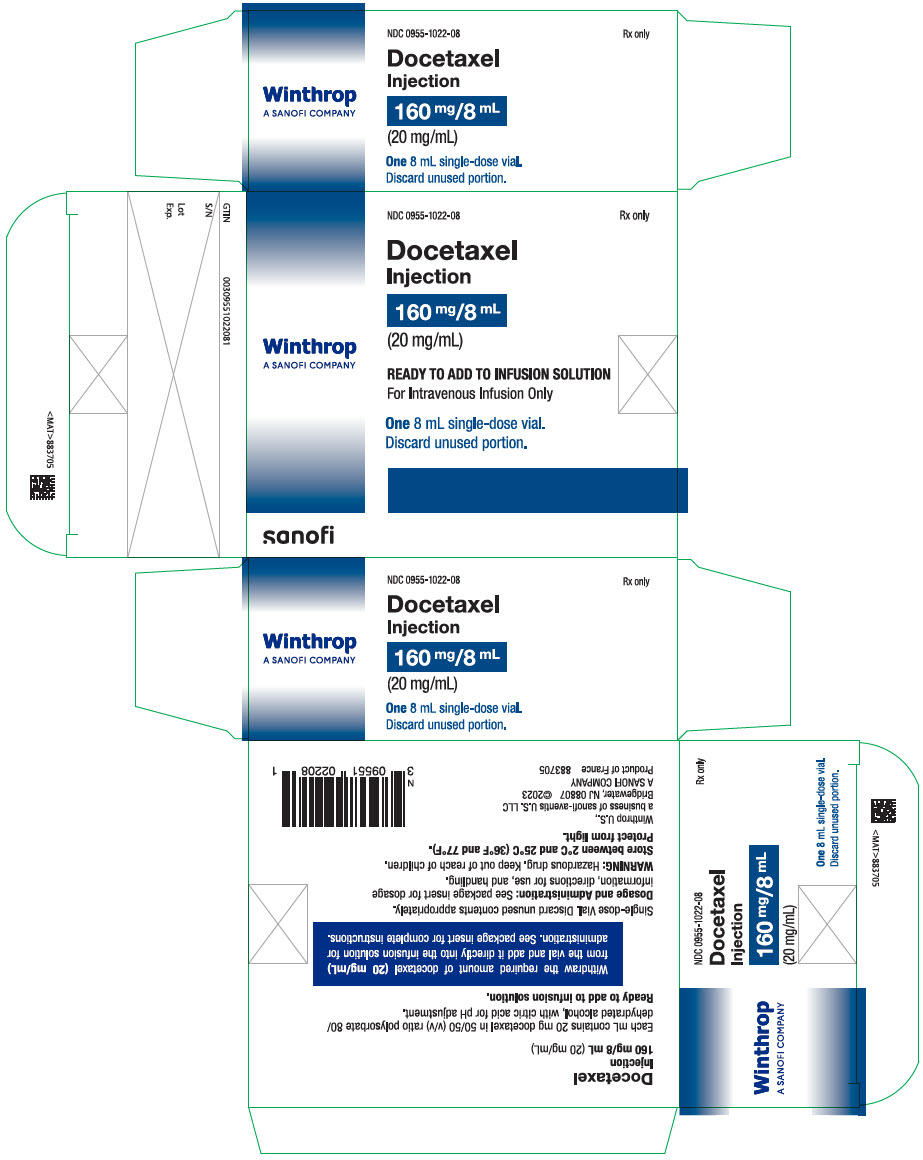 DRUG LABEL: Docetaxel
NDC: 0955-1021 | Form: INJECTION, SOLUTION, CONCENTRATE
Manufacturer: Sanofi-Aventis U.S. LLC
Category: prescription | Type: HUMAN PRESCRIPTION DRUG LABEL
Date: 20241206

ACTIVE INGREDIENTS: DOCETAXEL 80 mg/4 mL
INACTIVE INGREDIENTS: POLYSORBATE 80 2.16 g/4 mL; ALCOHOL 1.58 g/4 mL

HIGHLIGHTS OF PRESCRIBING INFORMATION

These highlights do not include all the information needed to use DOCETAXEL safely and effectively. See full prescribing information for DOCETAXEL.
DOCETAXEL injection, for intravenous use
Initial U.S. Approval: 1996

WARNING: TOXIC DEATHS, HEPATOTOXICITY, NEUTROPENIA, HYPERSENSITIVITY REACTIONS, and FLUID RETENTION

See full prescribing information for complete boxed warning.

- Treatment-related mortality increases with abnormal liver function, at higher doses, and in patients with NSCLC and prior platinum-based therapy receiving Docetaxel at 100 mg/m^2(5.1)
- Avoid use of Docetaxel if bilirubin > ULN, or if AST and/or ALT >1.5 × ULN concomitant with alkaline phosphatase >2.5 × ULN. LFT elevations increase risk of severe or life-threatening complications. Obtain LFTs before each treatment cycle (5.2)
- Do not administer Docetaxel to patients with neutrophil counts <1500 cells/mm^3. Obtain frequent blood counts to monitor for neutropenia (4, 5.3)
- Severe hypersensitivity, including fatal anaphylaxis, has been reported in patients who received dexamethasone premedication. Severe reactions require immediate discontinuation of docetaxel and administration of appropriate therapy (5.5)
- Contraindicated if history of severe hypersensitivity reactions to Docetaxel or to drugs formulated with polysorbate 80 (4)
- Severe fluid retention may occur despite dexamethasone (5.6)

1 INDICATIONS AND USAGE

Docetaxel is a microtubule inhibitor indicated for:

- Breast Cancer (BC): single agent for locally advanced or metastatic BC after chemotherapy failure; and with doxorubicin and cyclophosphamide as adjuvant treatment of operable node-positive BC (1.1)
- Non-small Cell Lung Cancer (NSCLC): single agent for locally advanced or metastatic NSCLC after platinum therapy failure; and with cisplatin for unresectable, locally advanced or metastatic untreated NSCLC (1.2)
- Castration-Resistant Prostate Cancer (CRPC): with prednisone in metastatic castration-resistant prostate cancer (1.3)
- Gastric Adenocarcinoma (GC): with cisplatin and fluorouracil for untreated, advanced GC, including the gastroesophageal junction (1.4)
- Squamous Cell Carcinoma of the Head and Neck (SCCHN): with cisplatin and fluorouracil for induction treatment of locally advanced SCCHN (1.5)

2 DOSAGE AND ADMINISTRATION

Administer in a facility equipped to manage possible complications (e.g., anaphylaxis). Administer intravenously (IV) over 1 hr every 3 weeks. PVC equipment is not recommended. Use only a 21 gauge needle to withdraw Docetaxel from the vial.

- BC locally advanced or metastatic: 60 mg/m^2to 100 mg/m^2single agent (2.1)
- BC adjuvant: 75 mg/m^2administered 1 hour after doxorubicin 50 mg/m^2and cyclophosphamide 500 mg/m^2every 3 weeks for 6 cycles (2.1)
- NSCLC: after platinum therapy failure: 75 mg/m^2single agent (2.2)
- NSCLC: chemotherapy naive: 75 mg/m^2followed by cisplatin 75 mg/m^2(2.2)
- HRPC: 75 mg/m^2with 5 mg prednisone twice a day continuously (2.3)
- GC: 75 mg/m^2followed by cisplatin 75 mg/m^2(both on day 1 only) followed by fluorouracil 750 mg/m^2per day as a 24-hr IV (days 1–5), starting at end of cisplatin infusion (2.4)
- SCCHN: 75 mg/m^2followed by cisplatin 75 mg/m^2IV (day 1), followed by fluorouracil 750 mg/m^2per day as a 24-hr IV (days 1–5), starting at end of cisplatin infusion; for 4 cycles (2.5)
- SCCHN: 75 mg/m^2followed by cisplatin 100 mg/m^2IV (day 1), followed by fluorouracil 1000 mg/m^2per day as a 24-hr IV (days 1–4); for 3 cycles (2.5)

For all patients:

- Premedicate with oral corticosteroids (2.6)
- Adjust dose as needed (2.7)

3 DOSAGE FORMS AND STRENGTHS

- Injection: One-vial Docetaxel: Single-dose vials 20 mg/mL, 80 mg/4 mL and 160 mg/8 mL (3)

4 CONTRAINDICATIONS

- Hypersensitivity to docetaxel or polysorbate 80 (4)
- Neutrophil counts of <1500 cells/mm^3(4)

5 WARNINGS AND PRECAUTIONS

- Second primary malignancies: In patients treated with Docetaxel-containing regimens, monitor for delayed AML, MDS, NHL, and renal cancer. (5.7)
- Cutaneous reactions: Reactions including erythema of the extremities with edema followed by desquamation may occur. Severe cutaneous adverse reactions have been reported. Severe skin toxicity may require dose adjustment or permanent treatment discontinuation. (5.8)
- Neurologic reactions: Reactions including paresthesia, dysesthesia, and pain may occur. Severe neurosensory symptoms require dose adjustment or discontinuation if persistent. (5.9)
- Eye disorders: Cystoid macular edema (CME) has been reported and requires treatment discontinuation. (5.10)
- Asthenia: Severe asthenia may occur and may require treatment discontinuation. (5.11)
- Embryo-fetal toxicity: Can cause fetal harm. Advise patients of the potential risk to a fetus and to use effective contraception. (5.12, 8.1, 8.3)
- Alcohol content: The alcohol content in a dose of Docetaxel injection may affect the central nervous system. This may include impairment of a patient's ability to drive or use machines immediately after infusion. (5.13)
- Tumor lysis syndrome: Tumor lysis syndrome has been reported. Patients at risk should be well hydrated and closely monitored during treatment. (5.14)

6 ADVERSE REACTIONS

Most common adverse reactions across all Docetaxel indications are infections, neutropenia, anemia, febrile neutropenia, hypersensitivity, thrombocytopenia, neuropathy, dysgeusia, dyspnea, constipation, anorexia, nail disorders, fluid retention, asthenia, pain, nausea, diarrhea, vomiting, mucositis, alopecia, skin reactions, and myalgia. (6)

To report SUSPECTED ADVERSE REACTIONS, contact sanofi-aventis U.S. LLC at 1-800-633-1610 or FDA at 1-800-FDA-1088 or www.fda.gov/medwatch.

7 DRUG INTERACTIONS

- Cytochrome P450 3A4 inducers, inhibitors, or substrates: May alter docetaxel metabolism. (7)

8 USE IN SPECIFIC POPULATIONS

- Lactation: Advise women not to breastfeed. (8.2)
- Females and Males of Reproductive Potential: Verify pregnancy status of females prior to initiation of Docetaxel. (8.3)

FULL PRESCRIBING INFORMATION

WARNING: TOXIC DEATHS, HEPATOTOXICITY, NEUTROPENIA, HYPERSENSITIVITY REACTIONS, and FLUID RETENTION

Treatment-related mortality associated with Docetaxel therapy is increased in patients with abnormal liver function, in patients receiving higher doses, and in patients with non-small cell lung carcinoma and a history of prior treatment with platinum-based chemotherapy who receive Docetaxel as a single agent at a dose of 100 mg/m^2 [see Warnings and Precautions (5.1)] .

Avoid the use of Docetaxel in patients with bilirubin > upper limit of normal (ULN), or to patients with AST and/or ALT >1.5 × ULN concomitant with alkaline phosphatase >2.5 × ULN. Patients with elevations of bilirubin or abnormalities of transaminase concurrent with alkaline phosphatase are at increased risk for the development of severe neutropenia, febrile neutropenia, infections, severe thrombocytopenia, severe stomatitis, severe skin toxicity, and toxic death. Patients with isolated elevations of transaminase >1.5 × ULN also had a higher rate of febrile neutropenia. Measure bilirubin, AST or ALT, and alkaline phosphatase prior to each cycle of Docetaxel [see Warnings and Precautions (5.2)] .

Do not administer Docetaxel to patients with neutrophil counts of <1500 cells/mm^3. Monitor blood counts frequently as neutropenia may be severe and result in infection [see Warnings and Precautions (5.3)] .

Do not administer Docetaxel to patients who have a history of severe hypersensitivity reactions to Docetaxel or to other drugs formulated with polysorbate 80 [see Contraindications (4)] . Severe hypersensitivity reactions have been reported in patients despite dexamethasone premedication. Hypersensitivity reactions require immediate discontinuation of the Docetaxel infusion and administration of appropriate therapy [see Warnings and Precautions (5.5)] .

Severe fluid retention occurred in 6.5% (6/92) of patients despite use of dexamethasone premedication. It was characterized by one or more of the following events: poorly tolerated peripheral edema, generalized edema, pleural effusion requiring urgent drainage, dyspnea at rest, cardiac tamponade, or pronounced abdominal distention (due to ascites) [see Warnings and Precautions (5.6)] .

1 INDICATIONS AND USAGE

1.1 Breast Cancer

Docetaxel is indicated for the treatment of patients with locally advanced or metastatic breast cancer after failure of prior chemotherapy.

Docetaxel in combination with doxorubicin and cyclophosphamide is indicated for the adjuvant treatment of patients with operable node-positive breast cancer.

1.2 Non-small Cell Lung Cancer

Docetaxel as a single agent is indicated for the treatment of patients with locally advanced or metastatic non-small cell lung cancer after failure of prior platinum-based chemotherapy.

Docetaxel in combination with cisplatin is indicated for the treatment of patients with unresectable, locally advanced or metastatic non-small cell lung cancer who have not previously received chemotherapy for this condition.

1.3 Prostate Cancer

Docetaxel in combination with prednisone is indicated for the treatment of patients with metastatic castration-resistant prostate cancer.

1.4 Gastric Adenocarcinoma

Docetaxel in combination with cisplatin and fluorouracil is indicated for the treatment of patients with advanced gastric adenocarcinoma, including adenocarcinoma of the gastroesophageal junction, who have not received prior chemotherapy for advanced disease.

1.5 Head and Neck Cancer

Docetaxel in combination with cisplatin and fluorouracil is indicated for the induction treatment of patients with locally advanced squamous cell carcinoma of the head and neck (SCCHN).

2 DOSAGE AND ADMINISTRATION

For all indications, toxicities may warrant dosage adjustments [see Dosage and Administration (2.7)] .

Administer in a facility equipped to manage possible complications (e.g., anaphylaxis).

2.1 Breast Cancer

- For locally advanced or metastatic breast cancer after failure of prior chemotherapy, the recommended dose of docetaxel is 60 mg/m^2to 100 mg/m^2administered intravenously over 1 hour every 3 weeks.
- For the adjuvant treatment of operable node-positive breast cancer, the recommended docetaxel dose is 75 mg/m^2administered 1 hour after doxorubicin 50 mg/m^2and cyclophosphamide 500 mg/m^2every 3 weeks for 6 courses. Prophylactic G-CSF may be used to mitigate the risk of hematological toxicities [see Dosage and Administration (2.7)] .

2.2 Non-small Cell Lung Cancer

- For treatment after failure of prior platinum-based chemotherapy, docetaxel was evaluated as monotherapy, and the recommended dose is 75 mg/m^2administered intravenously over 1 hour every 3 weeks. A dose of 100 mg/m^2in patients previously treated with chemotherapy was associated with increased hematologic toxicity, infection, and treatment-related mortality in randomized controlled trials [see Boxed Warning, Dosage and Administration (2.7), Warnings and Precautions (5), Clinical Studies (14)] .
- For chemotherapy-naive patients, docetaxel was evaluated in combination with cisplatin. The recommended dose of docetaxel is 75 mg/m^2administered intravenously over 1 hour immediately followed by cisplatin 75 mg/m^2over 30–60 minutes every 3 weeks [see Dosage and Administration (2.7)] .

2.3 Prostate Cancer

- For metastatic castration-resistant prostate cancer, the recommended dose of docetaxel is 75 mg/m^2every 3 weeks as a 1 hour intravenous infusion. Prednisone 5 mg orally twice daily is administered continuously [see Dosage and Administration (2.7)] .

2.4 Gastric Adenocarcinoma

- For gastric adenocarcinoma, the recommended dose of docetaxel is 75 mg/m^2as a 1 hour intravenous infusion, followed by cisplatin 75 mg/m^2, as a 1 to 3 hour intravenous infusion (both on day 1 only), followed by fluorouracil 750 mg/m^2per day given as a 24-hour continuous intravenous infusion for 5 days, starting at the end of the cisplatin infusion. Treatment is repeated every three weeks. Patients must receive premedication with antiemetics and appropriate hydration for cisplatin administration [see Dosage and Administration (2.7)] .

2.5 Head and Neck Cancer

Patients must receive premedication with antiemetics, and appropriate hydration (prior to and after cisplatin administration). Prophylaxis for neutropenic infections should be administered. All patients treated on the docetaxel containing arms of the TAX323 and TAX324 studies received prophylactic antibiotics.

Induction Chemotherapy Followed by Radiotherapy (TAX323)

For the induction treatment of locally advanced inoperable SCCHN, the recommended dose of docetaxel is 75 mg/m^2as a 1 hour intravenous infusion followed by cisplatin 75 mg/m^2intravenously over 1 hour, on day one, followed by fluorouracil as a continuous intravenous infusion at 750 mg/m^2per day for five days. This regimen is administered every 3 weeks for 4 cycles. Following chemotherapy, patients should receive radiotherapy [see Dosage and Administration (2.7)] .

Induction Chemotherapy Followed by Chemoradiotherapy (TAX324)

For the induction treatment of patients with locally advanced (unresectable, low surgical cure, or organ preservation) SCCHN, the recommended dose of docetaxel is 75 mg/m^2as a 1 hour intravenous infusion on day 1, followed by cisplatin 100 mg/m^2administered as a 30-minute to 3 hour infusion, followed by fluorouracil 1000 mg/m^2/day as a continuous infusion from day 1 to day 4. This regimen is administered every 3 weeks for 3 cycles. Following chemotherapy, patients should receive chemoradiotherapy [see Dosage and Administration (2.7)] .

2.6 Premedication Regimen

All patients should be premedicated with oral corticosteroids (see below for prostate cancer) such as dexamethasone 16 mg per day (e.g., 8 mg twice daily) for 3 days starting 1 day prior to docetaxel administration in order to reduce the incidence and severity of fluid retention as well as the severity of hypersensitivity reactions [see Boxed Warning, Warnings and Precautions (5.5)] .

For metastatic castration-resistant prostate cancer, given the concurrent use of prednisone, the recommended premedication regimen is oral dexamethasone 8 mg at 12 hours, 3 hours, and 1 hour before the docetaxel infusion [see Warnings and Precautions (5.5)] .

2.7 Dosage Adjustments during Treatment

Breast Cancer

Patients who are dosed initially at 100 mg/m^2and who experience either febrile neutropenia, neutrophils <500 cells/mm^3for more than 1 week, or severe or cumulative cutaneous reactions during docetaxel therapy should have the dosage adjusted from 100 mg/m^2to 75 mg/m^2. If the patient continues to experience these reactions, the dosage should either be decreased from 75 mg/m^2to 55 mg/m^2or the treatment should be discontinued. Conversely, patients who are dosed initially at 60 mg/m^2and who do not experience febrile neutropenia, neutrophils <500 cells/mm^3for more than 1 week, severe or cumulative cutaneous reactions, or severe peripheral neuropathy during docetaxel therapy may tolerate higher doses. Patients who develop ≥grade 3 peripheral neuropathy should have docetaxel treatment discontinued entirely.

Combination Therapy with Docetaxel in the Adjuvant Treatment of Breast Cancer

Docetaxel in combination with doxorubicin and cyclophosphamide should be administered when the neutrophil count is ≥1,500 cells/mm^3. Patients who experience febrile neutropenia should receive G-CSF in all subsequent cycles. Patients who continue to experience this reaction should remain on G-CSF and have their docetaxel dose reduced to 60 mg/m^2. Patients who experience grade 3 or 4 stomatitis should have their docetaxel dose decreased to 60 mg/m^2. Patients who experience severe or cumulative cutaneous reactions or moderate neurosensory signs and/or symptoms during docetaxel therapy should have their dosage of docetaxel reduced from 75 mg/m^2to 60 mg/m^2. If the patient continues to experience these reactions at 60 mg/m^2, treatment should be discontinued.

Non-small Cell Lung Cancer

Monotherapy with docetaxel for NSCLC treatment after failure of prior platinum-based chemotherapy

Patients who are dosed initially at 75 mg/m^2and who experience either febrile neutropenia, neutrophils <500 cells/mm^3for more than one week, severe or cumulative cutaneous reactions, or other grade 3/4 non-hematological toxicities during docetaxel treatment should have treatment withheld until resolution of the toxicity and then resumed at 55 mg/m^2. Patients who develop ≥grade 3 peripheral neuropathy should have docetaxel treatment discontinued entirely.

Combination therapy with docetaxel for chemotherapy-naive NSCLC

For patients who are dosed initially at docetaxel 75 mg/m^2in combination with cisplatin, and whose nadir of platelet count during the previous course of therapy is <25,000 cells/mm^3, in patients who experience febrile neutropenia, and in patients with serious non-hematologic toxicities, the docetaxel dosage in subsequent cycles should be reduced to 65 mg/m^2. In patients who require a further dose reduction, a dose of 50 mg/m^2is recommended. For cisplatin dosage adjustments, see manufacturers' prescribing information.

Prostate Cancer

Combination therapy with Docetaxel for metastatic castration-resistant prostate cancer

Docetaxel should be administered when the neutrophil count is ≥1,500 cells/mm^3. Patients who experience either febrile neutropenia, neutrophils <500 cells/mm^3for more than one week, severe or cumulative cutaneous reactions or moderate neurosensory signs and/or symptoms during docetaxel therapy should have the dosage of docetaxel reduced from 75 mg/m^2to 60 mg/m^2. If the patient continues to experience these reactions at 60 mg/m^2, the treatment should be discontinued.

Gastric or Head and Neck Cancer

Docetaxel in combination with cisplatin and fluorouracil in gastric cancer or head and neck cancer

Patients treated with docetaxel in combination with cisplatin and fluorouracil must receive antiemetics and appropriate hydration according to current institutional guidelines. In both studies, G-CSF was recommended during the second and/or subsequent cycles in case of febrile neutropenia, or documented infection with neutropenia, or neutropenia lasting more than 7 days. If an episode of febrile neutropenia, prolonged neutropenia or neutropenic infection occurs despite G-CSF use, the docetaxel dose should be reduced from 75 mg/m^2to 60 mg/m^2. If subsequent episodes of complicated neutropenia occur the docetaxel dose should be reduced from 60 mg/m^2to 45 mg/m^2. In case of grade 4 thrombocytopenia the docetaxel dose should be reduced from 75 mg/m^2to 60 mg/m^2. Do not retreat patients with subsequent cycles of docetaxel until neutrophils recover to a level >1,500 cells/mm^3 [see Contraindications (4)] . Avoid retreating patients until platelets recover to a level >100,000 cells/mm^3. Discontinue treatment if these toxicities persist [see Warnings and Precautions (5.3)] .

Recommended dose modifications for toxicities in patients treated with docetaxel in combination with cisplatin and fluorouracil are shown in Table 1.

Table 1: Recommended Dose Modifications for Toxicities in Patients Treated with Docetaxel in Combination with Cisplatin and Fluorouracil
Toxicity | Dosage adjustment
Diarrhea grade 3 | First episode: reduce fluorouracil dose by 20%. Second episode: then reduce docetaxel dose by 20%.
Diarrhea grade 4 | First episode: reduce docetaxel and fluorouracil doses by 20%. Second episode: discontinue treatment.
Stomatitis/mucositis grade 3 | First episode: reduce fluorouracil dose by 20%. Second episode: stop fluorouracil only, at all subsequent cycles. Third episode: reduce docetaxel dose by 20%.
Stomatitis/mucositis grade 4 | First episode: stop fluorouracil only, at all subsequent cycles. Second episode: reduce docetaxel dose by 20%.

Liver dysfunction:

In case of AST/ALT >2.5 to ≤5 × ULN and AP ≤2.5 × ULN, or AST/ALT >1.5 to ≤5 × ULN and AP >2.5 to ≤5 × ULN, docetaxel should be reduced by 20%.

In case of AST/ALT >5 × ULN and/or AP >5 × ULN docetaxel should be stopped.

The dose modifications for cisplatin and fluorouracil in the gastric cancer study are provided below.

Cisplatin dose modifications and delays

Peripheral neuropathy: A neurological examination should be performed before entry into the study, and then at least every 2 cycles and at the end of treatment. In the case of neurological signs or symptoms, more frequent examinations should be performed and the following dose modifications can be made according to NCI-CTCAE grade:

- Grade 2: Reduce cisplatin dose by 20%.
- Grade 3: Discontinue treatment.

Ototoxicity: In the case of grade 3 toxicity, discontinue treatment.

Nephrotoxicity: In the event of a rise in serum creatinine ≥grade 2 (>1.5 × normal value) despite adequate rehydration, CrCl should be determined before each subsequent cycle and the following dose reductions should be considered (see Table 2).

For other cisplatin dosage adjustments, also refer to the manufacturers' prescribing information.

Table 2: Dose Reductions for Evaluation of Creatinine Clearance
Creatinine clearance result before next cycle | Cisplatin dose next cycle
CrCl ≥60 mL/min | Full dose of cisplatin was given. CrCl was to be repeated before each treatment cycle.
CrCl between 40 and 59 mL/min | Dose of cisplatin was reduced by 50% at subsequent cycle. If CrCl was >60 mL/min at end of cycle, full cisplatin dose was reinstituted at the next cycle. If no recovery was observed, then cisplatin was omitted from the next treatment cycle.
CrCl <40 mL/min | Dose of cisplatin was omitted in that treatment cycle only. If CrCl was still <40 mL/min at the end of cycle, cisplatin was discontinued. If CrCl was >40 and <60 mL/min at end of cycle, a 50% cisplatin dose was given at the next cycle. If CrCl was >60 mL/min at end of cycle, full cisplatin dose was given at next cycle.
CrCl = Creatinine clearance

Fluorouracil dose modifications and treatment delays

For diarrhea and stomatitis, see Table 1.

In the event of grade 2 or greater plantar-palmar toxicity, fluorouracil should be stopped until recovery. The fluorouracil dosage should be reduced by 20%.

For other greater than grade 3 toxicities, except alopecia and anemia, chemotherapy should be delayed (for a maximum of 2 weeks from the planned date of infusion) until resolution to grade ≤1 and then recommenced, if medically appropriate.

For other fluorouracil dosage adjustments, also refer to the manufacturers' prescribing information.

Combination Therapy with Strong CYP3A4 Inhibitors

Avoid using concomitant strong CYP3A4 inhibitors (e.g., ketoconazole, itraconazole, clarithromycin, atazanavir, indinavir, nefazodone, nelfinavir, ritonavir, saquinavir, telithromycin and voriconazole). There are no clinical data with a dose adjustment in patients receiving strong CYP3A4 inhibitors. Based on extrapolation from a pharmacokinetic study with ketoconazole in 7 patients, consider a 50% docetaxel dose reduction if patients require coadministration of a strong CYP3A4 inhibitor [see Drug Interactions (7), Clinical Pharmacology (12.3)] .

2.8 Administration Precautions

Docetaxel is a hazardous anticancer drug and, as with other potentially toxic compounds, caution should be exercised when handling and preparing docetaxel solutions. The use of gloves is recommended [see How Supplied/Storage and Handling (16.3)] .

If Docetaxel injection initial diluted solution, or final dilution for infusion should come into contact with the skin, immediately and thoroughly wash with soap and water. If Docetaxel injection initial diluted solution, or final dilution for infusion should come into contact with mucosa, immediately and thoroughly wash with water.

Contact of the docetaxel with plasticized PVC equipment or devices used to prepare solutions for infusion is not recommended. In order to minimize patient exposure to the plasticizer DEHP (di-2-ethylhexyl phthalate), which may be leached from PVC infusion bags or sets, the final docetaxel dilution for infusion should be stored in bottles (glass, polypropylene) or plastic bags (polypropylene, polyolefin) and administered through polyethylene-lined administration sets.

One-vial Docetaxel (Injection)

Docetaxel injection requires NO prior dilution with a diluent and is ready to add to the infusion solution.

Please follow the preparation instructions provided below.

2.9 Preparation and Administration

DO NOT use the two-vial formulation (Injection and diluent) with the one-vial formulation.

One-vial Docetaxel (Injection)

Docetaxel injection (20 mg/mL) requires NO prior dilution with a diluent and is ready to add to the infusion solution. Use only a 21-gauge needle to withdraw docetaxel from the vial because larger bore needles (e.g., 18 and 19 gauge) may result in stopper coring and rubber particulates.

1. Docetaxel vials should be stored between 2°C and 25°C (36°F and 77°F). If the vials are stored under refrigeration, allow the appropriate number of vials of Docetaxel injection vials to stand at room temperature for approximately 5 minutes before use.
2. Using onlya 21-gauge needle, aseptically withdraw the required amount of Docetaxel injection (20 mg docetaxel/mL) with a calibrated syringe and inject via a single injection (one shot) into a 250 mL infusion bag or bottle of either 0.9% Sodium Chloride solution or 5% Dextrose solution to produce a final concentration of 0.3 mg/mL to 0.74 mg/mL.
  If a dose greater than 200 mg of docetaxel is required, use a larger volume of the infusion vehicle so that a concentration of 0.74 mg/mL docetaxel is not exceeded.
3. Thoroughly mix the infusion by gentle manual rotation.
4. As with all parenteral products, docetaxel should be inspected visually for particulate matter or discoloration prior to administration whenever the solution and container permit. If the docetaxel dilution for intravenous infusion is not clear or appears to have precipitation, it should be discarded.
5. Docetaxel infusion solution is supersaturated, therefore may crystallize over time. If crystals appear, the solution must no longer be used and shall be discarded.

The docetaxel dilution for infusion should be administered intravenously as a 1-hour infusion under ambient room temperature (below 25°C) and lighting conditions.

2.10 Stability

Docetaxel final dilution for infusion, if stored between 2°C and 25°C (36°F and 77°F) is stable for 6 hours. Docetaxel final dilution for infusion (in either 0.9% Sodium Chloride solution or 5% Dextrose solution) should be used within 6 hours (including the 1 hour intravenous administration).

In addition, physical and chemical in-use stability of the infusion solution prepared as recommended has been demonstrated in non-PVC bags up to 48 hours when stored between 2°C and 8°C (36°F and 46°F).

3 DOSAGE FORMS AND STRENGTHS

One-vial Docetaxel (Injection)

Docetaxel 20 mg/mL

Docetaxel injection 20 mg/1 mL single-dose vial: 20 mg docetaxel in 1 mL 50/50 (v/v) ratio polysorbate 80/dehydrated alcohol.

Docetaxel 80 mg/4 mL

Docetaxel injection 80 mg/4 mL single-dose vial: 80 mg docetaxel in 4 mL 50/50 (v/v) ratio polysorbate 80/dehydrated alcohol.

Docetaxel 160 mg/8 mL

Docetaxel injection 160 mg/8 mL single-dose vial: 160 mg docetaxel in 8 mL 50/50 (v/v) ratio polysorbate 80/dehydrated alcohol.

4 CONTRAINDICATIONS

Docetaxel is contraindicated in patients with:

- neutrophil counts of <1500 cells/mm^3 [see Warnings and Precautions (5.3)] .
- a history of severe hypersensitivity reactions to docetaxel or to other drugs formulated with polysorbate 80. Severe reactions, including anaphylaxis, have occurred [see Warnings and Precautions (5.5)] .

5 WARNINGS AND PRECAUTIONS

5.1 Toxic Deaths

Breast Cancer

Docetaxel administered at 100 mg/m^2was associated with deaths considered possibly or probably related to treatment in 2.0% (19/965) of metastatic breast cancer patients, both previously treated and untreated, with normal baseline liver function and in 11.5% (7/61) of patients with various tumor types who had abnormal baseline liver function (AST and/or ALT >1.5 times ULN together with AP >2.5 times ULN). Among patients dosed at 60 mg/m^2, mortality related to treatment occurred in 0.6% (3/481) of patients with normal liver function, and in 3 of 7 patients with abnormal liver function. Approximately half of these deaths occurred during the first cycle. Sepsis accounted for the majority of the deaths.

Non-small Cell Lung Cancer

Docetaxel administered at a dose of 100 mg/m^2in patients with locally advanced or metastatic non-small cell lung cancer who had a history of prior platinum-based chemotherapy was associated with increased treatment-related mortality (14% and 5% in two randomized, controlled studies). There were 2.8% treatment-related deaths among the 176 patients treated at the 75 mg/m^2dose in the randomized trials. Among patients who experienced treatment-related mortality at the 75 mg/m^2dose level, 3 of 5 patients had an ECOG PS of 2 at study entry [see Dosage and Administration (2.2), Clinical Studies (14)] .

5.2 Hepatic Impairment

Patients with elevations of bilirubin or abnormalities of transaminase concurrent with alkaline phosphatase are at increased risk for the development of severe neutropenia, febrile neutropenia, infections, severe thrombocytopenia, severe stomatitis, severe skin toxicity, and toxic death.

Avoid docetaxel in patients with bilirubin > upper limit of normal (ULN), or to patients with AST and/or ALT >1.5 × ULN concomitant with alkaline phosphatase >2.5 × ULN [see Warnings and Precautions (5.1)] .

For patients with isolated elevations of transaminase >1.5 × ULN, consider docetaxel dose modifications [see Dosage and Administration (2.7)] .

Measure bilirubin, AST or ALT, and alkaline phosphatase prior to each cycle of docetaxel therapy.

5.3 Hematologic Effects

Perform frequent peripheral blood cell counts on all patients receiving docetaxel. Do not retreat patients with subsequent cycles of docetaxel until neutrophils recover to a level >1500 cells/mm^3 [see Contraindications (4)] . Avoid retreating patients until platelets recover to a level >100,000 cells/mm^3.

A 25% reduction in the dose of docetaxel is recommended during subsequent cycles following severe neutropenia (<500 cells/mm^3) lasting 7 days or more, febrile neutropenia, or a grade 4 infection in a docetaxel cycle [see Dosage and Administration (2.7)] .

Neutropenia (<2000 neutrophils/mm^3) occurs in virtually all patients given 60 mg/m^2to 100 mg/m^2of docetaxel and grade 4 neutropenia (<500 cells/mm^3) occurs in 85% of patients given 100 mg/m^2and 75% of patients given 60 mg/m^2. Frequent monitoring of blood counts is, therefore, essential so that dose can be adjusted. Docetaxel should not be administered to patients with neutrophils <1500 cells/mm^3.

Febrile neutropenia occurred in about 12% of patients given 100 mg/m^2but was very uncommon in patients given 60 mg/m^2. Hematologic responses, febrile reactions and infections, and rates of septic death for different regimens are dose related [see Adverse Reactions (6.1), Clinical Studies (14)] .

Three breast cancer patients with severe liver impairment (bilirubin >1.7 times ULN) developed fatal gastrointestinal bleeding associated with severe drug-induced thrombocytopenia. In gastric cancer patients treated with docetaxel in combination with cisplatin and fluorouracil (TCF), febrile neutropenia and/or neutropenic infection occurred in 12% of patients receiving G-CSF compared to 28% who did not. Patients receiving TCF should be closely monitored during the first and subsequent cycles for febrile neutropenia and neutropenic infection [see Dosage and Administration (2.7), Adverse Reactions (6)] .

5.4 Enterocolitis and Neutropenic Colitis

Enterocolitis and neutropenic colitis (typhlitis) have occurred in patients treated with docetaxel alone and in combination with other chemotherapeutic agents, despite the coadministration of G-CSF. Caution is recommended for patients with neutropenia, particularly at risk for developing gastrointestinal complications. Enterocolitis and neutropenic enterocolitis may develop at any time, and could lead to death as early as the first day of symptom onset. Monitor patients closely from onset of any symptoms of gastrointestinal toxicity. Inform patients to contact their healthcare provider with new, or worsening symptoms of gastrointestinal toxicity [see Dosage and Administration (2), Warnings and Precautions (5.3), Adverse Reactions (6.2)] .

5.5 Hypersensitivity Reactions

Monitor patients closely for hypersensitivity reactions, especially during the first and second infusions. Severe hypersensitivity reactions characterized by generalized rash/erythema, hypotension and/or bronchospasm, or fatal anaphylaxis, have been reported in patients premedicated with 3 days of corticosteroids. Severe hypersensitivity reactions require immediate discontinuation of the docetaxel infusion and aggressive therapy. Do not rechallenge patients with a history of severe hypersensitivity reactions with docetaxel [see Contraindications (4)] .

Patients who have previously experienced a hypersensitivity reaction to paclitaxel may develop a hypersensitivity reaction to docetaxel that may include severe or fatal reactions such as anaphylaxis. Monitor patients with a previous history of hypersensitivity to paclitaxel closely during initiation of docetaxel therapy. Hypersensitivity reactions may occur within a few minutes following initiation of a docetaxel infusion. If minor reactions such as flushing or localized skin reactions occur, interruption of therapy is not required. All patients should be premedicated with an oral corticosteroid prior to the initiation of the infusion of docetaxel [see Dosage and Administration (2.6)] .

5.6 Fluid Retention

Severe fluid retention has been reported following docetaxel therapy. Patients should be premedicated with oral corticosteroids prior to each docetaxel administration to reduce the incidence and severity of fluid retention [see Dosage and Administration (2.6)] . Patients with pre-existing effusions should be closely monitored from the first dose for the possible exacerbation of the effusions.

When fluid retention occurs, peripheral edema usually starts in the lower extremities and may become generalized with a median weight gain of 2 kg.

Among 92 breast cancer patients premedicated with 3-day corticosteroids, moderate fluid retention occurred in 27.2% and severe fluid retention in 6.5%. The median cumulative dose to onset of moderate or severe fluid retention was 819 mg/m^2. Nine of 92 patients (9.8%) of patients discontinued treatment due to fluid retention: 4 patients discontinued with severe fluid retention; the remaining 5 had mild or moderate fluid retention. The median cumulative dose to treatment discontinuation due to fluid retention was 1021 mg/m^2. Fluid retention was completely, but sometimes slowly, reversible with a median of 16 weeks from the last infusion of docetaxel to resolution (range: 0 to 42+ weeks). Patients developing peripheral edema may be treated with standard measures, e.g., salt restriction, oral diuretic(s).

5.7 Second Primary Malignancies

Second primary malignancies, notably acute myeloid leukemia (AML), myelodysplastic syndrome (MDS), non-Hodgkin's lymphoma (NHL), and renal cancer, have been reported in patients treated with docetaxel-containing regimens. These adverse reactions may occur several months or years after docetaxel-containing therapy.

Treatment-related AML or MDS has occurred in patients given anthracyclines and/or cyclophosphamide, including use in adjuvant therapy for breast cancer. In the adjuvant breast cancer trial (TAX316) AML occurred in 3 of 744 patients who received docetaxel, doxorubicin and cyclophosphamide (TAC) and in 1 of 736 patients who received fluorouracil, doxorubicin, and cyclophosphamide [see Clinical Studies (14.2)] . In TAC-treated patients, the risk of delayed myelodysplasia or myeloid leukemia requires hematological follow-up. Monitor patients for second primary malignancies [see Adverse Reactions (6.1)] .

5.8 Cutaneous Reactions

Localized erythema of the extremities with edema followed by desquamation has been observed. In case of severe skin toxicity, an adjustment in dosage is recommended [see Dosage and Administration (2.7)] . The discontinuation rate due to skin toxicity was 1.6% (15/965) for metastatic breast cancer patients. Among 92 breast cancer patients premedicated with 3-day corticosteroids, there were no cases of severe skin toxicity reported and no patient discontinued docetaxel due to skin toxicity.

Severe cutaneous adverse reactions (SCARs) such as Stevens-Johnson syndrome (SJS), toxic epidermal necrolysis (TEN), and acute generalized exanthematous pustulosis (AGEP) have been reported in association with docetaxel treatment. Patients should be informed about the signs and symptoms of serious skin manifestations and monitored closely. Permanent treatment discontinuation should be considered in patients who experience SCARs.

5.9 Neurologic Reactions

Severe neurosensory symptoms (e.g. paresthesia, dysesthesia, pain) were observed in 5.5% (53/965) of metastatic breast cancer patients, and resulted in treatment discontinuation in 6.1%. When these symptoms occur, dosage must be adjusted. If symptoms persist, treatment should be discontinued [see Dosage and Administration (2.7)] . Patients who experienced neurotoxicity in clinical trials and for whom follow-up information on the complete resolution of the event was available had spontaneous reversal of symptoms with a median of 9 weeks from onset (range: 0 to 106 weeks). Severe peripheral motor neuropathy mainly manifested as distal extremity weakness occurred in 4.4% (42/965).

5.10 Eye Disorders

Cystoid macular edema (CME) has been reported in patients treated with docetaxel. Patients with impaired vision should undergo a prompt and comprehensive ophthalmologic examination. If CME is diagnosed, docetaxel treatment should be discontinued and appropriate treatment initiated. Alternative non-taxane cancer treatment should be considered.

5.11 Asthenia

Severe asthenia has been reported in 14.9% (144/965) of metastatic breast cancer patients but has led to treatment discontinuation in only 1.8%. Symptoms of fatigue and weakness may last a few days up to several weeks and may be associated with deterioration of performance status in patients with progressive disease.

5.12 Embryo-Fetal Toxicity

Based on findings from animal reproduction studies and its mechanism of action, docetaxel can cause fetal harm when administered to a pregnant woman [see Clinical Pharmacology (12.1)] . Available data from case reports in the literature and pharmacovigilance with docetaxel use in pregnant women are not sufficient to inform the drug-associated risk of major birth defects, miscarriage or adverse maternal or fetal outcomes. In animal reproduction studies, administration of docetaxel to pregnant rats and rabbits during the period of organogenesis caused embryo-fetal toxicities, including intrauterine mortality, at doses as low as 0.02 and 0.003 times the recommended human dose based on body surface area, respectively.

Advise pregnant women and females of reproductive potential of the potential risk to a fetus. Verify pregnancy status in females of reproductive potential prior to initiating docetaxel. Advise females of reproductive potential to use effective contraception during treatment and for 2 months after the last dose of docetaxel. Advise male patients with female partners of reproductive potential to use effective contraception during treatment and for 4 months after the last dose of docetaxel [see Use in Specific Populations (8.1, 8.3)] .

5.13 Alcohol Content

Cases of intoxication have been reported with some formulations of docetaxel due to the alcohol content. The alcohol content in a dose of Docetaxel injection may affect the central nervous system and should be taken into account for patients in whom alcohol intake should be avoided or minimized. Consideration should be given to the alcohol content in Docetaxel injection on the ability to drive or use machines immediately after the infusion. Each administration of Docetaxel injection at 100 mg/m^2delivers 2.0 g/m^2of ethanol. For a patient with a BSA of 2.0 m^2, this would deliver 4.0 grams of ethanol [see Description (11)] . Other docetaxel products may have a different amount of alcohol.

5.14 Tumor Lysis Syndrome

Tumor lysis syndrome has been reported with docetaxel [see Adverse Reactions (6.2)] . Patients at risk of tumor lysis syndrome (e.g., with renal impairment, hyperuricemia, bulky tumor) should be closely monitored prior to initiating docetaxel and periodically during treatment. Correction of dehydration and treatment of high uric acid levels are recommended prior to initiation of treatment.

6 ADVERSE REACTIONS

The most serious adverse reactions from docetaxel are:

- Toxic Deaths [see Boxed Warning, Warnings and Precautions (5.1)]
- Hepatic Impairment [see Boxed Warning, Warnings and Precautions (5.2)]
- Hematologic Effects [see Boxed Warning, Warnings and Precautions (5.3)]
- Enterocolitis and Neutropenic Colitis [see Warnings and Precautions (5.4)]
- Hypersensitivity Reactions [see Boxed Warning, Warnings and Precautions (5.5)]
- Fluid Retention [see Boxed Warning, Warnings and Precautions (5.6)]
- Second Primary Malignancies [see Warnings and Precautions (5.7)]
- Cutaneous Reactions [see Warnings and Precautions (5.8)]
- Neurologic Reactions [see Warnings and Precautions (5.9)]
- Eye Disorders [see Warnings and Precautions (5.10)]
- Asthenia [see Warnings and Precautions (5.11)]
- Alcohol Content [see Warnings and Precautions (5.13)]

The most common adverse reactions across all docetaxel indications are infections, neutropenia, anemia, febrile neutropenia, hypersensitivity, thrombocytopenia, neuropathy, dysgeusia, dyspnea, constipation, anorexia, nail disorders, fluid retention, asthenia, pain, nausea, diarrhea, vomiting, mucositis, alopecia, skin reactions, and myalgia. Incidence varies depending on the indication.

Adverse reactions are described according to indication. Because clinical trials are conducted under widely varying conditions, adverse reaction rates observed in the clinical trials of a drug cannot be directly compared to rates in the clinical trials of another drug and may not reflect the rates observed in practice.

Responding patients may not experience an improvement in performance status on therapy and may experience worsening. The relationship between changes in performance status, response to therapy, and treatment-related side effects has not been established.

6.1 Clinical Trials Experience

Breast Cancer

Monotherapy with docetaxel for locally advanced or metastatic breast cancer after failure of prior chemotherapy

Docetaxel 100 mg/m^2: Adverse drug reactions occurring in at least 5% of patients are compared for three populations who received docetaxel administered at 100 mg/m^2as a 1-hour infusion every 3 weeks: 2045 patients with various tumor types and normal baseline liver function tests; the subset of 965 patients with locally advanced or metastatic breast cancer, both previously treated and untreated with chemotherapy, who had normal baseline liver function tests; and an additional 61 patients with various tumor types who had abnormal liver function tests at baseline. These reactions were described using COSTART terms and were considered possibly or probably related to docetaxel. At least 95% of these patients did not receive hematopoietic support. The safety profile is generally similar in patients receiving docetaxel for the treatment of breast cancer and in patients with other tumor types. (See Table 3.)

Table 3: Summary of Adverse Reactions in Patients Receiving Docetaxel at 100 mg/m^2
Adverse Reaction | All Tumor Types Normal LFTs [Normal Baseline LFTs: Transaminases ≤1.5 times ULN or alkaline phosphatase ≤2.5 times ULN or isolated elevations of transaminases or alkaline phosphatase up to 5 times ULN] n=2045 % | All Tumor Types Elevated LFTs [Elevated Baseline LFTs: AST and/or ALT >1.5 times ULN concurrent with alkaline phosphatase >2.5 times ULN] n=61 % | Breast Cancer Normal LFTs n=965 %
Hematologic
Neutropenia
<2000 cells/mm^3 | 96 | 96 | 99
<500 cells/mm^3 | 75 | 88 | 86
Leukopenia
<4000 cells/mm^3 | 96 | 98 | 99
<1000 cells/mm^3 | 32 | 47 | 44
Thrombocytopenia
<100,000 cells/mm^3 | 8 | 25 | 9
Anemia
<11 g/dL | 90 | 92 | 94
<8 g/dL | 9 | 31 | 8
Febrile Neutropenia [Febrile Neutropenia: ANC grade 4 with fever >38°C with intravenous antibiotics and/or hospitalization] | 11 | 26 | 12
Septic Death | 2 | 5 | 1
Non-Septic Death | 1 | 7 | 1
Infections
Any | 22 | 33 | 22
Severe | 6 | 16 | 6
Fever in Absence of Infection
Any | 31 | 41 | 35
Severe | 2 | 8 | 2
Hypersensitivity Reactions
Regardless of Premedication
Any | 21 | 20 | 18
Severe | 4 | 10 | 3
With 3-day Premedication | n=92 | n=3 | n=92
Any | 15 | 33 | 15
Severe | 2 | 0 | 2
Fluid Retention
Regardless of Premedication
Any | 47 | 39 | 60
Severe | 7 | 8 | 9
With 3-day Premedication | n=92 | n=3 | n=92
Any | 64 | 67 | 64
Severe | 7 | 33 | 7
Neurosensory
Any | 49 | 34 | 58
Severe | 4 | 0 | 6
Cutaneous
Any | 48 | 54 | 47
Severe | 5 | 10 | 5
Nail Changes
Any | 31 | 23 | 41
Severe | 3 | 5 | 4
Gastrointestinal
Nausea | 39 | 38 | 42
Vomiting | 22 | 23 | 23
Diarrhea | 39 | 33 | 43
Severe | 5 | 5 | 6
Stomatitis
Any | 42 | 49 | 52
Severe | 6 | 13 | 7
Alopecia | 76 | 62 | 74
Asthenia
Any | 62 | 53 | 66
Severe | 13 | 25 | 15
Myalgia
Any | 19 | 16 | 21
Severe | 2 | 2 | 2
Arthralgia | 9 | 7 | 8
Infusion Site Reactions | 4 | 3 | 4

Hematologic reactions

Reversible marrow suppression was the major dose-limiting toxicity of docetaxel [see Warnings and Precautions (5.3)] . The median time to nadir was 7 days, while the median duration of severe neutropenia (<500 cells/mm^3) was 7 days. Among 2045 patients with solid tumors and normal baseline LFTs, severe neutropenia occurred in 75.4% and lasted for more than 7 days in 2.9% of cycles.

Febrile neutropenia (<500 cells/mm^3with fever >38°C with intravenous antibiotics and/or hospitalization) occurred in 11% of patients with solid tumors, in 12.3% of patients with metastatic breast cancer, and in 9.8% of 92 breast cancer patients premedicated with 3-day corticosteroids.

Severe infectious episodes occurred in 6.1% of patients with solid tumors, in 6.4% of patients with metastatic breast cancer, and in 5.4% of 92 breast cancer patients premedicated with 3-day corticosteroids.

Thrombocytopenia (<100,000 cells/mm^3) associated with fatal gastrointestinal hemorrhage has been reported.

Hypersensitivity reactions

Severe hypersensitivity reactions have been reported [see Boxed Warning, Warnings and Precautions (5.5)] . Minor events, including flushing, rash with or without pruritus, chest tightness, back pain, dyspnea, drug fever, or chills, have been reported and resolved after discontinuing the infusion and instituting appropriate therapy.

Fluid retention

Fluid retention can occur with the use of docetaxel [see Boxed Warning, Dosage and Administration (2.6), Warnings and Precautions (5.6)] .

Cutaneous reactions

Severe skin toxicity is discussed elsewhere in the label [see Warnings and Precautions (5.8)] . Reversible cutaneous reactions characterized by a rash including localized eruptions, mainly on the feet and/or hands, but also on the arms, face, or thorax, usually associated with pruritus, have been observed. Eruptions generally occurred within 1 week after docetaxel infusion, recovered before the next infusion, and were not disabling.

Severe nail disorders were characterized by hypo or hyperpigmentation, and occasionally by onycholysis (in 0.8% of patients with solid tumors) and pain.

Neurologic reactions

Neurologic reactions are discussed elsewhere in the label [see Warnings and Precautions (5.9)] .

Gastrointestinal reactions

Nausea, vomiting, and diarrhea were generally mild to moderate. Severe reactions occurred in 3%–5% of patients with solid tumors and to a similar extent among metastatic breast cancer patients. The incidence of severe reactions was 1% or less for the 92 breast cancer patients premedicated with 3-day corticosteroids.

Severe stomatitis occurred in 5.5% of patients with solid tumors, in 7.4% of patients with metastatic breast cancer, and in 1.1% of the 92 breast cancer patients premedicated with 3-day corticosteroids.

Cardiovascular reactions

Hypotension occurred in 2.8% of patients with solid tumors; 1.2% required treatment. Clinically meaningful events such as heart failure, sinus tachycardia, atrial flutter, dysrhythmia, unstable angina, pulmonary edema, and hypertension have occurred. Seven of 86 (8.1%) of metastatic breast cancer patients receiving docetaxel 100 mg/m^2in a randomized trial and who had serial left ventricular ejection fractions assessed developed deterioration of LVEF by ≥10% associated with a drop below the institutional lower limit of normal.

Infusion site reactions

Infusion site reactions were generally mild and consisted of hyperpigmentation, inflammation, redness or dryness of the skin, phlebitis, extravasation, or swelling of the vein.

Hepatic reactions

In patients with normal LFTs at baseline, bilirubin values greater than the ULN occurred in 8.9% of patients. Increases in AST or ALT >1.5 times the ULN, or alkaline phosphatase >2.5 times ULN, were observed in 18.9% and 7.3% of patients, respectively. While on docetaxel, increases in AST and/or ALT >1.5 times ULN concomitant with alkaline phosphatase >2.5 times ULN occurred in 4.3% of patients with normal LFTs at baseline. Whether these changes were related to the drug or underlying disease has not been established.

Hematologic and other toxicity: Relation to dose and baseline liver chemistry abnormalities

Hematologic and other toxicity is increased at higher doses and in patients with elevated baseline liver function tests (LFTs). In the following tables, adverse drug reactions are compared for three populations: 730 patients with normal LFTs given docetaxel at 100 mg/m^2in the randomized and single arm studies of metastatic breast cancer after failure of previous chemotherapy; 18 patients in these studies who had abnormal baseline LFTs (defined as AST and/or ALT >1.5 times ULN concurrent with alkaline phosphatase >2.5 times ULN); and 174 patients in Japanese studies given docetaxel at 60 mg/m^2who had normal LFTs (see Tables 4and 5).

Table 4: Hematologic Adverse Reactions in Breast Cancer Patients Previously Treated with Chemotherapy Treated at Docetaxel 100 mg/m^2with Normal or Elevated Liver Function Tests or 60 mg/m^2with Normal Liver Function Tests
 |  | Docetaxel 100 mg/m^2 |  | Docetaxel 60 mg/m^2
Adverse Reaction |  | Normal LFTs [Normal Baseline LFTs: Transaminases ≤1.5 times ULN or alkaline phosphatase ≤2.5 times ULN or isolated elevations of transaminases or alkaline phosphatase up to 5 times ULN] n=730 % | Elevated LFTs [Elevated Baseline LFTs: AST and/or ALT >1.5 times ULN concurrent with alkaline phosphatase >2.5 times ULN] n=18 % | Normal LFTs n=174 %
Neutropenia
Any | <2000 cells/mm^3 | 98 | 100 | 95
Grade 4 | <500 cells/mm^3 | 84 | 94 | 75
Thrombocytopenia
Any | <100,000 cells/mm^3 | 11 | 44 | 14
Grade 4 | <20,000 cells/mm^3 | 1 | 17 | 1
Anemia | <11 g/dL | 95 | 94 | 65
Infection [Incidence of infection requiring hospitalization and/or intravenous antibiotics was 8.5% (n=62) among the 730 patients with normal LFTs at baseline; 7 patients had concurrent grade 3 neutropenia, and 46 patients had grade 4 neutropenia.]
Any |  | 23 | 39 | 1
Grade 3 and 4 |  | 7 | 33 | 0
Febrile Neutropenia [Febrile Neutropenia: For 100 mg/m 2, ANC grade 4 and fever >38°C with intravenous antibiotics and/or hospitalization; for 60 mg/m 2, ANC grade 3/4 and fever >38.1°C]
By Patient |  | 12 | 33 | 0
By Course |  | 2 | 9 | 0
Septic Death |  | 2 | 6 | 1
Non-Septic Death |  | 1 | 11 | 0

Table 5: Non-hematologic Adverse Reactions in Breast Cancer Patients Previously Treated with Chemotherapy Treated at Docetaxel 100 mg/m^2with Normal or Elevated Liver Function Tests or 60 mg/m^2with Normal Liver Function Tests
 | Docetaxel 100 mg/m^2 |  | Docetaxel 60 mg/m^2
Adverse Reaction | Normal LFTs [Normal Baseline LFTs: Transaminases ≤1.5 times ULN or alkaline phosphatase ≤2.5 times ULN or isolated elevations of transaminases or alkaline phosphatase up to 5 times ULN] n=730 % | Elevated LFTs [Elevated Baseline Liver Function: AST and/or ALT >1.5 times ULN concurrent with alkaline phosphatase >2.5 times ULN] n=18 % | Normal LFTs n=174 %
Acute Hypersensitivity
Reaction Regardless of Premedication
Any | 13 | 6 | 1
Severe | 1 | 0 | 0
Fluid Retention [Fluid Retention includes (by COSTART): edema (peripheral, localized, generalized, lymphedema, pulmonary edema, and edema otherwise not specified) and effusion (pleural, pericardial, and ascites); no premedication given with the 60 mg/m 2 dose]
Regardless of Premedication
Any | 56 | 61 | 13
Severe | 8 | 17 | 0
Neurosensory
Any | 57 | 50 | 20
Severe | 6 | 0 | 0
Myalgia | 23 | 33 | 3
Cutaneous
Any | 45 | 61 | 31
Severe | 5 | 17 | 0
Asthenia
Any | 65 | 44 | 66
Severe | 17 | 22 | 0
Diarrhea
Any | 42 | 28 | NA
Severe | 6 | 11
Stomatitis
Any | 53 | 67 | 19
Severe | 8 | 39 | 1
NA = not available

In the three-arm monotherapy trial, TAX313, which compared docetaxel 60 mg/m^2, 75 mg/m^2and 100 mg/m^2in advanced breast cancer, grade 3/4 or severe adverse reactions occurred in 49.0% of patients treated with docetaxel 60 mg/m^2compared to 55.3% and 65.9% treated with 75 mg/m^2and 100 mg/m^2, respectively. Discontinuation due to adverse reactions was reported in 5.3% of patients treated with 60 mg/m^2versus 6.9% and 16.5% for patients treated at 75 and 100 mg/m^2, respectively. Deaths within 30 days of last treatment occurred in 4.0% of patients treated with 60 mg/m^2compared to 5.3% and 1.6% for patients treated at 75 mg/m^2and 100 mg/m^2, respectively.

The following adverse reactions were associated with increasing docetaxel doses: fluid retention (26%, 38%, and 46% at 60 mg/m^2, 75 mg/m^2, and 100 mg/m^2, respectively), thrombocytopenia (7%, 11% and 12%, respectively), neutropenia (92%, 94%, and 97%, respectively), febrile neutropenia (5%, 7%, and 14%, respectively), treatment-related grade 3/4 infection (2%, 3%, and 7%, respectively) and anemia (87%, 94%, and 97%, respectively).

Combination therapy with docetaxel in the adjuvant treatment of breast cancer

The following table presents treatment-emergent adverse reactions observed in 744 patients, who were treated with docetaxel 75 mg/m^2every 3 weeks in combination with doxorubicin and cyclophosphamide (see Table 6).

Table 6: Clinically Important Treatment-Emergent Adverse Reactions Regardless of Causal Relationship in Patients Receiving Docetaxel in Combination with Doxorubicin and Cyclophosphamide (TAX316)
 | Docetaxel 75 mg/m^2+ Doxorubicin 50 mg/m^2+ Cyclophosphamide 500 mg/m^2(TAC) n=744 % |  | Fluorouracil 500 mg/m^2+ Doxorubicin 50 mg/m^2+ Cyclophosphamide 500 mg/m^2(FAC) n=736 %
Adverse Reaction | Any | Grade 3/4 | Any | Grade 3/4
Anemia | 92 | 4 | 72 | 2
Neutropenia | 71 | 66 | 82 | 49
Fever in absence of infection | 47 | 1 | 17 | 0
Infection | 39 | 4 | 36 | 2
Thrombocytopenia | 39 | 2 | 28 | 1
Febrile neutropenia | 25 | N/A | 3 | N/A
Neutropenic infection | 12 | N/A | 6 | N/A
Hypersensitivity reactions | 13 | 1 | 4 | 0
Lymphedema | 4 | 0 | 1 | 0
Fluid Retention [COSTART term and grading system for events related to treatment.] | 35 | 1 | 15 | 0
Peripheral edema | 27 | 0 | 7 | 0
Weight gain | 13 | 0 | 9 | 0
Neuropathy sensory | 26 | 0 | 10 | 0
Neuro-cortical | 5 | 1 | 6 | 1
Neuropathy motor | 4 | 0 | 2 | 0
Neuro-cerebellar | 2 | 0 | 2 | 0
Syncope | 2 | 1 | 1 | 0
Alopecia | 98 | N/A | 97 | N/A
Skin toxicity | 27 | 1 | 18 | 0
Nail disorders | 19 | 0 | 14 | 0
Nausea | 81 | 5 | 88 | 10
Stomatitis | 69 | 7 | 53 | 2
Vomiting | 45 | 4 | 59 | 7
Diarrhea | 35 | 4 | 28 | 2
Constipation | 34 | 1 | 32 | 1
Taste perversion | 28 | 1 | 15 | 0
Anorexia | 22 | 2 | 18 | 1
Abdominal Pain | 11 | 1 | 5 | 0
Amenorrhea | 62 | N/A | 52 | N/A
Cough | 14 | 0 | 10 | 0
Cardiac dysrhythmias | 8 | 0 | 6 | 0
Vasodilatation | 27 | 1 | 21 | 1
Hypotension | 2 | 0 | 1 | 0
Phlebitis | 1 | 0 | 1 | 0
Asthenia | 81 | 11 | 71 | 6
Myalgia | 27 | 1 | 10 | 0
Arthralgia | 19 | 1 | 9 | 0
Lacrimation disorder | 11 | 0 | 7 | 0
Conjunctivitis | 5 | 0 | 7 | 0

Of the 744 patients treated with TAC, 36.3% experienced severe treatment-emergent adverse reactions compared to 26.6% of the 736 patients treated with FAC. Dose reductions due to hematologic toxicity occurred in 1% of cycles in the TAC arm versus 0.1% of cycles in the FAC arm. Six percent of patients treated with TAC discontinued treatment due to adverse reactions, compared to 1.1% treated with FAC; fever in the absence of infection and allergy being the most common reasons for withdrawal among TAC-treated patients. Two patients died in each arm within 30 days of their last study treatment; 1 death per arm was attributed to study drugs.

Fever and infection

During the treatment period, fever in the absence of infection was seen in 46.5% of TAC-treated patients and in 17.1% of FAC-treated patients. Grade 3/4 fever in the absence of infection was seen in 1.3% and 0% of TAC and FAC-treated patients, respectively. Infection was seen in 39.4% of TAC-treated patients compared to 36.3% of FAC-treated patients. Grade 3/4 infection was seen in 3.9% and 2.2% of TAC-treated and FAC-treated patients, respectively. There were no septic deaths in either treatment arm during the treatment period.

Gastrointestinal reactions

In addition to gastrointestinal reactions reflected in the table above, 7 patients in the TAC arm were reported to have colitis/enteritis/large intestine perforation versus one patient in the FAC arm. Five of the 7 TAC-treated patients required treatment discontinuation; no deaths due to these events occurred during the treatment period.

Cardiovascular reactions

More cardiovascular reactions were reported in the TAC arm versus the FAC arm during the treatment period: arrhythmias, all grades (6.2% vs 4.9%), and hypotension, all grades (1.9% vs 0.8%). Twenty-six (26) patients (3.5%) in the TAC arm and 17 patients (2.3%) in the FAC arm developed CHF during the study period. All except one patient in each arm were diagnosed with CHF during the follow-up period. Two (2) patients in TAC arm and 4 patients in FAC arm died due to CHF. The risk of CHF was higher in the TAC arm in the first year, and then was similar in both treatment arms.

Adverse reactions during the follow-up period (median follow-up time of 8 years)

In study TAX316, the most common adverse reactions that started during the treatment period and persisted into the follow-up period in TAC and FAC patients are described below (median follow-up time of 8 years).

Nervous system disorders

In study TAX316, peripheral sensory neuropathy started during the treatment period and persisted into the follow-up period in 84 patients (11.3%) in TAC arm and 15 patients (2%) in FAC arm. At the end of the follow-up period (median follow-up time of 8 years), peripheral sensory neuropathy was observed to be ongoing in 10 patients (1.3%) in TAC arm, and in 2 patients (0.3%) in FAC arm.

Skin and subcutaneous tissue disorders

In study TAX316, alopecia persisting into the follow-up period after the end of chemotherapy was reported in 687 of 744 TAC patients (92.3%) and 645 of 736 FAC patients (87.6%). At the end of the follow-up period (actual median follow-up time of 8 years), alopecia was observed to be ongoing in 29 TAC patients (3.9%) and 16 FAC patients (2.2%).

Reproductive system and breast disorders

In study TAX316, amenorrhea that started during the treatment period and persisted into the follow-up period after the end of chemotherapy was reported in 202 of 744 TAC patients (27.2%) and 125 of 736 FAC patients (17.0%). Amenorrhea was observed to be ongoing at the end of the follow-up period (median follow-up time of 8 years) in 121 of 744 TAC patients (16.3%) and 86 FAC patients (11.7%).

General disorders and administration site conditions

In study TAX316, peripheral edema that started during the treatment period and persisted into the follow-up period after the end of chemotherapy was observed in 119 of 744 TAC patients (16.0%) and 23 of 736 FAC patients (3.1%). At the end of the follow-up period (actual median follow-up time of 8 years), peripheral edema was ongoing in 19 TAC patients (2.6%) and 4 FAC patients (0.5%).

In study TAX316, lymphedema that started during the treatment period and persisted into the follow-up period after the end of chemotherapy was reported in 11 of 744 TAC patients (1.5%) and 1 of 736 FAC patients (0.1%). At the end of the follow-up period (actual median follow-up time of 8 years), lymphedema was observed to be ongoing in 6 TAC patients (0.8%) and 1 FAC patient (0.1%).

In study TAX316, asthenia that started during the treatment period and persisted into the follow-up period after the end of chemotherapy was reported in 236 of 744 TAC patients (31.7%) and 180 of 736 FAC patients (24.5%). At the end of the follow-up period (actual median follow-up time of 8 years), asthenia was observed to be ongoing in 29 TAC patients (3.9%) and 16 FAC patients (2.2%).

Acute myeloid leukemia (AML)/Myelodysplastic syndrome (MDS)

AML occurred in the adjuvant breast cancer trial (TAX316). The cumulative risk of developing treatment-related AML at median follow-up time of 8 years in TAX316 was 0.4% for TAC-treated patients and 0.1% for FAC-treated patients. One TAC patient (0.1%) and 1 FAC patient (0.1%) died due to AML during the follow-up period (median follow-up time of 8 years). Myelodysplastic syndrome occurred in 2 of 744 (0.3%) patients who received TAC and in 1 of 736 (0.1%) patients who received FAC. AML occurs at a higher frequency when these agents are given in combination with radiation therapy.

Lung Cancer

Monotherapy with docetaxel for unresectable, locally advanced or metastatic NSCLC previously treated with platinum-based chemotherapy

Docetaxel 75 mg/m^2: Treatment-emergent adverse drug reactions are shown in Table 7. Included in this table are safety data for a total of 176 patients with non-small cell lung carcinoma and a history of prior treatment with platinum-based chemotherapy who were treated in two randomized, controlled trials. These reactions were described using NCI Common Toxicity Criteria regardless of relationship to study treatment, except for the hematologic toxicities or where otherwise noted.

Table 7: Treatment-Emergent Adverse Reactions Regardless of Relationship to Treatment in Patients Receiving Docetaxel as Monotherapy for Non-small Cell Lung Cancer Previously Treated with Platinum-Based Chemotherapy [Normal Baseline LFTs: Transaminases ≤1.5 times ULN or alkaline phosphatase ≤2.5 times ULN or isolated elevations of transaminases or alkaline phosphatase up to 5 times ULN]
Adverse Reaction | Docetaxel 75 mg/m^2 n=176 % | Best Supportive Care n=49 % | Vinorelbine/Ifosfamide n=119 %
Neutropenia
Any | 84 | 14 | 83
Grade 3/4 | 65 | 12 | 57
Leukopenia
Any | 84 | 6 | 89
Grade 3/4 | 49 | 0 | 43
Thrombocytopenia
Any | 8 | 0 | 8
Grade 3/4 | 3 | 0 | 2
Anemia
Any | 91 | 55 | 91
Grade 3/4 | 9 | 12 | 14
Febrile
Neutropenia [Febrile Neutropenia: ANC grade 4 with fever >38°C with intravenous antibiotics and/or hospitalization] | 6 | NA [Not Applicable] | 1
Infection
Any | 34 | 29 | 30
Grade 3/4 | 10 | 6 | 9
Treatment Related Mortality | 3 | NA | 3
Hypersensitivity Reactions
Any | 6 | 0 | 1
Grade 3/4 | 3 | 0 | 0
Fluid Retention
Any | 34 | ND [Not Done] | 23
Severe | 3 |  | 3
Neurosensory
Any | 23 | 14 | 29
Grade 3/4 | 2 | 6 | 5
Neuromotor
Any | 16 | 8 | 10
Grade 3/4 | 5 | 6 | 3
Skin
Any | 20 | 6 | 17
Grade 3/4 | 1 | 2 | 1
Gastrointestinal
Nausea
Any | 34 | 31 | 31
Grade 3/4 | 5 | 4 | 8
Vomiting
Any | 22 | 27 | 22
Grade 3/4 | 3 | 2 | 6
Diarrhea
Any | 23 | 6 | 12
Grade 3/4 | 3 | 0 | 4
Alopecia | 56 | 35 | 50
Asthenia
Any | 53 | 57 | 54
Severe [COSTART term and grading system] | 18 | 39 | 23
Stomatitis
Any | 26 | 6 | 8
Grade 3/4 | 2 | 0 | 1
Pulmonary
Any | 41 | 49 | 45
Grade 3/4 | 21 | 29 | 19
Nail Disorder
Any | 11 | 0 | 2
Severe | 1 | 0 | 0
Myalgia
Any | 6 | 0 | 3
Severe | 0 | 0 | 0
Arthralgia
Any | 3 | 2 | 2
Severe | 0 | 0 | 1
Taste Perversion
Any | 6 | 0 | 0
Severe | 1 | 0 | 0

Combination therapy with docetaxel in chemotherapy-naive advanced unresectable or metastatic NSCLC

Table 8presents safety data from two arms of an open label, randomized controlled trial (TAX326) that enrolled patients with unresectable stage IIIB or IV non-small cell lung cancer and no history of prior chemotherapy. Adverse reactions were described using the NCI Common Toxicity Criteria except where otherwise noted.

Table 8: Adverse Reactions Regardless of Relationship to Treatment in Chemotherapy-Naive Advanced Non-small Cell Lung Cancer Patients Receiving Docetaxel in Combination with Cisplatin
Adverse Reaction | Docetaxel 75 mg/m^2+ Cisplatin 75 mg/m^2 n=406 % | Vinorelbine 25 mg/m^2+ Cisplatin 100 mg/m^2 n=396 %
Neutropenia
Any | 91 | 90
Grade 3/4 | 74 | 78
Febrile Neutropenia | 5 | 5
Thrombocytopenia
Any | 15 | 15
Grade 3/4 | 3 | 4
Anemia
Any | 89 | 94
Grade 3/4 | 7 | 25
Infection
Any | 35 | 37
Grade 3/4 | 8 | 8
Fever in absence of infection
Any | 33 | 29
Grade 3/4 | <1 | 1
Hypersensitivity Reaction [Replaces NCI term "Allergy"]
Any | 12 | 4
Grade 3/4 | 3 | <1
Fluid Retention [COSTART term and grading system]
Any | 54 | 42
All severe or life-threatening events | 2 | 2
Pleural effusion
Any | 23 | 22
All severe or life-threatening events | 2 | 2
Peripheral edema
Any | 34 | 18
All severe or life-threatening events | <1 | <1
Weight gain
Any | 15 | 9
All severe or life-threatening events | <1 | <1
Neurosensory
Any | 47 | 42
Grade 3/4 | 4 | 4
Neuromotor
Any | 19 | 17
Grade 3/4 | 3 | 6
Skin
Any | 16 | 14
Grade 3/4 | <1 | 1
Nausea
Any | 72 | 76
Grade 3/4 | 10 | 17
Vomiting
Any | 55 | 61
Grade 3/4 | 8 | 16
Diarrhea
Any | 47 | 25
Grade 3/4 | 7 | 3
Anorexia
Any | 42 | 40
All severe or life-threatening events | 5 | 5
Stomatitis
Any | 24 | 21
Grade 3/4 | 2 | 1
Alopecia
Any | 75 | 42
Grade 3 | <1 | 0
Asthenia
Any | 74 | 75
All severe or life-threatening events | 12 | 14
Nail Disorder
Any | 14 | <1
All severe events | <1 | 0
Myalgia
Any | 18 | 12
All severe events | <1 | <1

Deaths within 30 days of last study treatment occurred in 31 patients (7.6%) in the docetaxel+cisplatin arm and 37 patients (9.3%) in the vinorelbine+cisplatin arm. Deaths within 30 days of last study treatment attributed to study drug occurred in 9 patients (2.2%) in the docetaxel+cisplatin arm and 8 patients (2.0%) in the vinorelbine+cisplatin arm.

The second comparison in the study, vinorelbine+cisplatin versus docetaxel+carboplatin (which did not demonstrate a superior survival associated with docetaxel [see Clinical Studies (14.3)]) demonstrated a higher incidence of thrombocytopenia, diarrhea, fluid retention, hypersensitivity reactions, skin toxicity, alopecia and nail changes on the docetaxel+carboplatin arm, while a higher incidence of anemia, neurosensory toxicity, nausea, vomiting, anorexia and asthenia was observed on the vinorelbine+cisplatin arm.

Prostate Cancer

Combination therapy with docetaxel in patients with prostate cancer

The following data are based on the experience of 332 patients, who were treated with docetaxel 75 mg/m^2every 3 weeks in combination with prednisone 5 mg orally twice daily (see Table 9).

Table 9: Clinically Important Treatment-Emergent Adverse Reactions (Regardless of Relationship) in Patients with Prostate Cancer Who Received Docetaxel in Combination with Prednisone (TAX327)
 | Docetaxel 75 mg/m^2every 3 weeks + prednisone 5 mg twice daily n=332 % |  | Mitoxantrone 12 mg/m^2every 3 weeks + prednisone 5 mg twice daily n=335 %
Adverse Reaction | Any | Grade 3/4 | Any | Grade 3/4
Anemia | 67 | 5 | 58 | 2
Neutropenia | 41 | 32 | 48 | 22
Thrombocytopenia | 3 | 1 | 8 | 1
Febrile neutropenia | 3 | N/A | 2 | N/A
Infection | 32 | 6 | 20 | 4
Epistaxis | 6 | 0 | 2 | 0
Allergic Reactions | 8 | 1 | 1 | 0
Fluid Retention [Related to treatment] | 24 | 1 | 5 | 0
Weight Gain | 8 | 0 | 3 | 0
Peripheral Edema | 18 | 0 | 2 | 0
Neuropathy Sensory | 30 | 2 | 7 | 0
Neuropathy Motor | 7 | 2 | 3 | 1
Rash/Desquamation | 6 | 0 | 3 | 1
Alopecia | 65 | N/A | 13 | N/A
Nail Changes | 30 | 0 | 8 | 0
Nausea | 41 | 3 | 36 | 2
Diarrhea | 32 | 2 | 10 | 1
Stomatitis/Pharyngitis | 20 | 1 | 8 | 0
Taste Disturbance | 18 | 0 | 7 | 0
Vomiting | 17 | 2 | 14 | 2
Anorexia | 17 | 1 | 14 | 0
Cough | 12 | 0 | 8 | 0
Dyspnea | 15 | 3 | 9 | 1
Cardiac left ventricular function | 10 | 0 | 22 | 1
Fatigue | 53 | 5 | 35 | 5
Myalgia | 15 | 0 | 13 | 1
Tearing | 10 | 1 | 2 | 0
Arthralgia | 8 | 1 | 5 | 1

Gastric Cancer

Combination therapy with docetaxel in gastric adenocarcinoma

Data in the following table are based on the experience of 221 patients with advanced gastric adenocarcinoma and no history of prior chemotherapy for advanced disease who were treated with docetaxel 75 mg/m^2in combination with cisplatin and fluorouracil (see Table 10).

Table 10: Clinically Important Treatment-Emergent Adverse Reactions Regardless of Relationship to Treatment in the Gastric Cancer Study
 | Docetaxel 75 mg/m^2+ cisplatin 75 mg/m^2+ fluorouracil 750 mg/m^2 n=221 |  | Cisplatin 100 mg/m^2+ fluorouracil 1000 mg/m^2 n=224
Adverse Reaction | Any % | Grade 3/4 % | Any % | Grade 3/4 %
Anemia | 97 | 18 | 93 | 26
Neutropenia | 96 | 82 | 83 | 57
Fever in the absence of infection | 36 | 2 | 23 | 1
Thrombocytopenia | 26 | 8 | 39 | 14
Infection | 29 | 16 | 23 | 10
Febrile neutropenia | 16 | N/A | 5 | N/A
Neutropenic infection | 16 | N/A | 10 | N/A
Allergic reactions | 10 | 2 | 6 | 0
Fluid retention [Related to treatment] | 15 | 0 | 4 | 0
Edema | 13 | 0 | 3 | 0
Lethargy | 63 | 21 | 58 | 18
Neurosensory | 38 | 8 | 25 | 3
Neuromotor | 9 | 3 | 8 | 3
Dizziness | 16 | 5 | 8 | 2
Alopecia | 67 | 5 | 41 | 1
Rash/itch | 12 | 1 | 9 | 0
Nail changes | 8 | 0 | 0 | 0
Skin desquamation | 2 | 0 | 0 | 0
Nausea | 73 | 16 | 76 | 19
Vomiting | 67 | 15 | 73 | 19
Anorexia | 51 | 13 | 54 | 12
Stomatitis | 59 | 21 | 61 | 27
Diarrhea | 78 | 20 | 50 | 8
Constipation | 25 | 2 | 34 | 3
Esophagitis/dysphagia/odynophagia | 16 | 2 | 14 | 5
Gastrointestinal pain/cramping | 11 | 2 | 7 | 3
Cardiac dysrhythmias | 5 | 2 | 2 | 1
Myocardial ischemia | 1 | 0 | 3 | 2
Tearing | 8 | 0 | 2 | 0
Altered hearing | 6 | 0 | 13 | 2
Clinically important treatment-emergent adverse reactions were determined based upon frequency, severity, and clinical impact of the adverse reaction.

Head and Neck Cancer

Combination therapy with docetaxel in head and neck cancer

Table 11summarizes the safety data obtained from patients that received induction chemotherapy with docetaxel 75 mg/m^2in combination with cisplatin and fluorouracil followed by radiotherapy (TAX323; 174 patients) or chemoradiotherapy (TAX324; 251 patients). The treatment regimens are described in Section 14.6.

Table 11: Clinically Important Treatment-Emergent Adverse Reactions (Regardless of Relationship) in Patients with SCCHN Receiving Induction Chemotherapy with Docetaxel in Combination with Cisplatin and Fluorouracil Followed by Radiotherapy (TAX323) or Chemoradiotherapy (TAX324)
 | TAX323 (n=355) |  |  |  | TAX324 (n=494)
 | Docetaxel arm (n=174) |  | Comparator arm (n=181) |  | Docetaxel arm (n=251) |  | Comparator arm (n=243)
Adverse Reaction (by Body System) | Any % | Grade 3/4 % | Any % | Grade 3/4 % | Any % | Grade 3/4 % | Any % | Grade 3/4 %
Neutropenia | 93 | 76 | 87 | 53 | 95 | 84 | 84 | 56
Anemia | 89 | 9 | 88 | 14 | 90 | 12 | 86 | 10
Thrombocytopenia | 24 | 5 | 47 | 18 | 28 | 4 | 31 | 11
Infection | 27 | 9 | 26 | 8 | 23 | 6 | 28 | 5
Febrile neutropenia [Febrile neutropenia: grade ≥2 fever concomitant with grade 4 neutropenia requiring intravenous antibiotics and/or hospitalization.] | 5 | N/A | 2 | N/A | 12 | N/A | 7 | N/A
Neutropenic infection | 14 | N/A | 8 | N/A | 12 | N/A | 8 | N/A
Cancer pain | 21 | 5 | 16 | 3 | 17 | 9 | 20 | 11
Lethargy | 41 | 3 | 38 | 3 | 61 | 5 | 56 | 10
Fever in the absence of infection | 32 | 1 | 37 | 0 | 30 | 4 | 28 | 3
Myalgia | 10 | 1 | 7 | 0 | 7 | 0 | 7 | 2
Weight loss | 21 | 1 | 27 | 1 | 14 | 2 | 14 | 2
Allergy | 6 | 0 | 3 | 0 | 2 | 0 | 0 | 0
Fluid retention [Related to treatment.] Edema only Weight gain only | 20 13 6 | 0 0 0 | 14 7 6 | 1 0 0 | 13 12 0 | 1 1 0 | 7 6 1 | 2 1 0
Dizziness | 2 | 0 | 5 | 1 | 16 | 4 | 15 | 2
Neurosensory | 18 | 1 | 11 | 1 | 14 | 1 | 14 | 0
Altered hearing | 6 | 0 | 10 | 3 | 13 | 1 | 19 | 3
Neuromotor | 2 | 1 | 4 | 1 | 9 | 0 | 10 | 2
Alopecia | 81 | 11 | 43 | 0 | 68 | 4 | 44 | 1
Rash/itch | 12 | 0 | 6 | 0 | 20 | 0 | 16 | 1
Dry skin | 6 | 0 | 2 | 0 | 5 | 0 | 3 | 0
Desquamation | 4 | 1 | 6 | 0 | 2 | 0 | 5 | 0
Nausea | 47 | 1 | 51 | 7 | 77 | 14 | 80 | 14
Stomatitis | 43 | 4 | 47 | 11 | 66 | 21 | 68 | 27
Vomiting | 26 | 1 | 39 | 5 | 56 | 8 | 63 | 10
Diarrhea | 33 | 3 | 24 | 4 | 48 | 7 | 40 | 3
Constipation | 17 | 1 | 16 | 1 | 27 | 1 | 38 | 1
Anorexia | 16 | 1 | 25 | 3 | 40 | 12 | 34 | 12
Esophagitis/dysphagia/ Odynophagia | 13 | 1 | 18 | 3 | 25 | 13 | 26 | 10
Taste, sense of smell altered | 10 | 0 | 5 | 0 | 20 | 0 | 17 | 1
Gastrointestinal pain/cramping | 8 | 1 | 9 | 1 | 15 | 5 | 10 | 2
Heartburn | 6 | 0 | 6 | 0 | 13 | 2 | 13 | 1
Gastrointestinal bleeding | 4 | 2 | 0 | 0 | 5 | 1 | 2 | 1
Cardiac dysrhythmia | 2 | 2 | 2 | 1 | 6 | 3 | 5 | 3
Venous [Includes superficial and deep vein thrombosis and pulmonary embolism] | 3 | 2 | 6 | 2 | 4 | 2 | 5 | 4
Ischemia myocardial | 2 | 2 | 1 | 0 | 2 | 1 | 1 | 1
Tearing | 2 | 0 | 1 | 0 | 2 | 0 | 2 | 0
Conjunctivitis | 1 | 0 | 1 | 0 | 1 | 0 | 0.4 | 0
Clinically important treatment-emergent adverse reactions based upon frequency, severity, and clinical impact.

6.2 Postmarketing Experience

The following adverse reactions have been identified from clinical trials and/or postmarketing surveillance. Because these reactions are reported from a population of uncertain size, it is not always possible to reliably estimate their frequency or establish a causal relationship to drug exposure.

Body as a whole: diffuse pain, chest pain, radiation recall phenomenon, injection site recall reaction (recurrence of skin reaction at a site of previous extravasation following administration of docetaxel at a different site) at the site of previous extravasation.

Cardiovascular: atrial fibrillation, deep vein thrombosis, ECG abnormalities, thrombophlebitis, pulmonary embolism, syncope, tachycardia, myocardial infarction. Ventricular arrhythmia including ventricular tachycardia, in patients treated with docetaxel in combination regimens including doxorubicin, 5-fluorouracil and/or cyclophosphamide may be associated with fatal outcome.

Cutaneous: cutaneous lupus erythematosus, bullous eruptions such as erythema multiforme and severe cutaneous adverse reactions (SCARs) such as Stevens-Johnson syndrome, toxic epidermal necrolysis and acute generalized exanthematous pustulosis, scleroderma-like changes (usually preceded by peripheral lymphedema), severe palmar-plantar erythrodysesthesia, and permanent alopecia.

Gastrointestinal: enterocolitis, including colitis, ischemic colitis, and neutropenic enterocolitis, which may be fatal. Abdominal pain, anorexia, constipation, duodenal ulcer, esophagitis, gastrointestinal hemorrhage, gastrointestinal perforation, intestinal obstruction, ileus, and dehydration as a consequence of gastrointestinal events.

Hearing: ototoxicity, hearing disorders and/or hearing loss, including during use with other ototoxic drugs.

Hematologic: bleeding episodes, disseminated intravascular coagulation (DIC), often in association with sepsis or multiorgan failure.

Hepatic: hepatitis, sometimes fatal, primarily in patients with pre-existing liver disorders.

Hypersensitivity: anaphylactic shock with fatal outcome in patients who received premedication. Severe hypersensitivity reactions with fatal outcome with docetaxel in patients who previously experienced hypersensitivity reactions to paclitaxel.

Metabolism and nutrition disorders: electrolyte imbalance, including hyponatremia, hypokalemia, hypomagnesemia, and hypocalcemia. Tumor lysis syndrome, sometimes fatal.

Neurologic: confusion, seizures or transient loss of consciousness, sometimes appearing during the infusion of the drug.

Ophthalmologic: conjunctivitis, lacrimation or lacrimation with or without conjunctivitis, cystoid macular edema (CME). Excessive tearing which may be attributable to lacrimal duct obstruction. Transient visual disturbances (flashes, flashing lights, scotomata), typically occurring during drug infusion and reversible upon discontinuation of the infusion, in association with hypersensitivity reactions.

Respiratory: dyspnea, acute pulmonary edema, acute respiratory distress syndrome/pneumonitis, interstitial lung disease, interstitial pneumonia, respiratory failure, and pulmonary fibrosis, which may be fatal. Radiation pneumonitis in patients receiving concomitant radiotherapy.

Renal: renal insufficiency and renal failure , the majority of cases were associated with concomitant nephrotoxic drugs.

Second primary malignancies: second primary malignancies, including AML, MDS, NHL, and renal cancer [see Warnings and Precautions (5.7)] .

Musculoskeletal disorder: myositis.

7 DRUG INTERACTIONS

Docetaxel is a CYP3A4 substrate. In vitrostudies have shown that the metabolism of docetaxel may be modified by the concomitant administration of compounds that induce, inhibit, or are metabolized by cytochrome P450 3A4.

In vivostudies showed that the exposure of docetaxel increased 2.2-fold when it was coadministered with ketoconazole, a potent inhibitor of CYP3A4. Protease inhibitors, particularly ritonavir, may increase the exposure of docetaxel. Concomitant use of docetaxel and drugs that inhibit CYP3A4 may increase exposure to docetaxel and should be avoided. In patients receiving treatment with docetaxel, close monitoring for toxicity and a docetaxel dose reduction could be considered if systemic administration of a potent CYP3A4 inhibitor cannot be avoided [see Dosage and Administration (2.7), Clinical Pharmacology (12.3)] .

8 USE IN SPECIFIC POPULATIONS

8.1 Pregnancy

Risk Summary

Based on findings in animal reproduction studies and its mechanism of action, docetaxel can cause fetal harm when administered to a pregnant woman [see Clinical Pharmacology (12.1)] .

Available data from case reports in the literature and pharmacovigilance with docetaxel use in pregnant women are not sufficient to inform the drug-associated risk of major birth defects, miscarriage, or adverse maternal or fetal outcomes. Docetaxel contains alcohol which can interfere with neurobehavioral development [see Clinical Considerations] . In animal reproductive studies, administration of docetaxel to pregnant rats and rabbits during the period of organogenesis caused an increased incidence of embryo-fetal toxicities, including intrauterine mortality, at doses as low as 0.02 and 0.003 times the recommended human dose based on body surface area, respectively [see Data] . Advise pregnant women and females of reproductive potential of the potential risk to a fetus.

The estimated background risk of major birth defects and miscarriage for the indicated populations is unknown. All pregnancies have a background risk of birth defect, miscarriage, or other adverse outcomes. In the U.S. general population, the estimated background risk of major birth defects and miscarriage in clinically recognized pregnancies is 2% to 4% and 15% to 20%, respectively.

Clinical Considerations

Docetaxel contains alcohol [see Warnings and Precautions (5.13)] . Published studies have demonstrated that alcohol is associated with fetal harm including central nervous system abnormalities, behavioral disorders, and impaired intellectual development.

Data

Animal data

Intravenous administration of ≥0.3 and 0.03 mg/kg/day docetaxel to pregnant rats and rabbits, respectively, during the period of organogenesis caused an increased incidence of intrauterine mortality, resorptions, reduced fetal weights, and fetal ossification delays. Maternal toxicity was also observed at these doses, which were approximately 0.02 and 0.003 times the daily maximum recommended human dose based on body surface area, respectively.

8.2 Lactation

Risk Summary

There is no information regarding the presence of docetaxel in human milk, or on its effects on milk production or the breastfed child. No lactation studies in animals have been conducted. Because of the potential for serious adverse reactions in a breastfed child, advise women not to breastfeed during treatment with docetaxel and for 1 week after the last dose.

8.3 Females and Males of Reproductive Potential

Based on findings in animals, Docetaxel can cause fetal harm when administered to a pregnant woman [see Use in Specific Populations (8.1)] .

Pregnancy Testing

Verify pregnancy status in females of reproductive potential prior to initiating docetaxel.

Contraception

Females

Based on genetic toxicity findings, advise females of reproductive potential to use effective contraception during treatment and for 2 months after the last dose of docetaxel.

Males

Based on genetic toxicity findings, advise male patients with female partners of reproductive potential to use effective contraception during treatment and for 4 months after the last dose of docetaxel.

Infertility

Based on findings in animal studies, docetaxel may impair fertility in males of reproductive potential [see Nonclinical Toxicology (13.1)] .

8.4 Pediatric Use

The alcohol content of Docetaxel injection should be taken into account when given to pediatric patients [see Warnings and Precautions (5.13)] .

The efficacy of docetaxel in pediatric patients as monotherapy or in combination has not been established. The overall safety profile of docetaxel in pediatric patients receiving monotherapy or TCF was consistent with the known safety profile in adults.

Docetaxel has been studied in a total of 289 pediatric patients: 239 in 2 trials with monotherapy and 50 in combination treatment with cisplatin and 5-fluorouracil (TCF).

Docetaxel Monotherapy

Docetaxel monotherapy was evaluated in a dose-finding phase 1 trial in 61 pediatric patients (median age 12.5 years, range 1–22 years) with a variety of refractory solid tumors. The recommended dose was 125 mg/m^2as a 1-hour intravenous infusion every 21 days. The primary dose limiting toxicity was neutropenia.

The recommended dose for docetaxel monotherapy was evaluated in a phase 2 single-arm trial in 178 pediatric patients (median age 12 years, range 1–26 years) with a variety of recurrent/refractory solid tumors. Efficacy was not established with tumor response rates ranging from one complete response (CR) (0.6%) in a patient with undifferentiated sarcoma to four partial responses (2.2%) seen in one patient each with Ewing Sarcoma, neuroblastoma, osteosarcoma, and squamous cell carcinoma.

Docetaxel in Combination

Docetaxel was studied in combination with cisplatin and 5-fluorouracil (TCF) versus cisplatin and 5-fluorouracil (CF) for the induction treatment of nasopharyngeal carcinoma (NPC) in pediatric patients prior to chemoradiation consolidation. Seventy-five patients (median age 16 years, range 9 to 21 years) were randomized (2:1) to docetaxel (75 mg/m^2) in combination with cisplatin (75 mg/m^2) and 5-fluorouracil (750 mg/m^2) (TCF) or to cisplatin (80 mg/m^2) and 5-fluorouracil (1000 mg/m^2/day) (CF). The primary endpoint was the CR rate following induction treatment of NPC. One patient out of 50 in the TCF group (2%) had a complete response while none of the 25 patients in the CF group had a complete response.

Pharmacokinetics

Pharmacokinetic parameters for docetaxel were determined in 2 pediatric solid tumor trials. Following docetaxel administration at 55 mg/m^2to 235 mg/m^2in a 1-hour intravenous infusion every 3 weeks in 25 patients aged 1 to 20 years (median 11 years), docetaxel clearance was 17.3±10.9 L/h/m^2.

Docetaxel was administered in combination with cisplatin and 5-fluorouracil (TCF), at dose levels of 75 mg/m^2in a 1-hour intravenous infusion day 1 in 28 patients aged 10 to 21 years (median 16 years, 17 patients were older than 16). Docetaxel clearance was 17.9±8.75 L/h/m^2, corresponding to an AUC of 4.20±2.57 μg∙h/mL.

In summary, the body surface area adjusted clearance of docetaxel monotherapy and TCF combination in children were comparable to those in adults [see Clinical Pharmacology (12.3)] .

8.5 Geriatric Use

In general, dose selection for an elderly patient should be cautious, reflecting the greater frequency of decreased hepatic, renal, or cardiac function and of concomitant disease or other drug therapy in elderly patients.

Non-small Cell Lung Cancer

In a study conducted in chemotherapy-naive patients with NSCLC (TAX326), 148 patients (36%) in the docetaxel+cisplatin group were 65 years of age or greater. There were 128 patients (32%) in the vinorelbine+cisplatin group 65 years of age or greater. In the docetaxel+cisplatin group, patients less than 65 years of age had a median survival of 10.3 months (95% CI: 9.1 months, 11.8 months) and patients 65 years or older had a median survival of 12.1 months (95% CI: 9.3 months, 14 months). In patients 65 years of age or greater treated with docetaxel+cisplatin, diarrhea (55%), peripheral edema (39%) and stomatitis (28%) were observed more frequently than in the vinorelbine+cisplatin group (diarrhea 24%, peripheral edema 20%, stomatitis 20%). Patients treated with docetaxel+cisplatin who were 65 years of age or greater were more likely to experience diarrhea (55%), infections (42%), peripheral edema (39%) and stomatitis (28%) compared to patients less than the age of 65 administered the same treatment (43%, 31%, 31% and 21%, respectively).

When docetaxel was combined with carboplatin for the treatment of chemotherapy-naive, advanced non-small cell lung carcinoma, patients 65 years of age or greater (28%) experienced higher frequency of infection compared to similar patients treated with docetaxel+cisplatin, and a higher frequency of diarrhea, infection and peripheral edema than elderly patients treated with vinorelbine+cisplatin.

Prostate Cancer

Of the 333 patients treated with docetaxel every three weeks plus prednisone in the prostate cancer study (TAX327), 209 patients were 65 years of age or greater and 68 patients were older than 75 years. In patients treated with docetaxel every three weeks, the following treatment-emergent adverse reactions occurred at rates ≥10% higher in patients 65 years of age or greater compared to younger patients: anemia (71% vs 59%), infection (37% vs 24%), nail changes (34% vs 23%), anorexia (21% vs 10%), weight loss (15% vs 5%), respectively.

Breast Cancer

In the adjuvant breast cancer trial (TAX316), docetaxel in combination with doxorubicin and cyclophosphamide was administered to 744 patients of whom 48 (6%) were 65 years of age or greater. The number of elderly patients who received this regimen was not sufficient to determine whether there were differences in safety and efficacy between elderly and younger patients.

Gastric Cancer

Among the 221 patients treated with docetaxel in combination with cisplatin and fluorouracil in the gastric cancer study, 54 were 65 years of age or older and 2 patients were older than 75 years. In this study, the number of patients who were 65 years of age or older was insufficient to determine whether they respond differently from younger patients. However, the incidence of serious adverse reactions was higher in the elderly patients compared to younger patients. The incidence of the following adverse reactions (all grades, regardless of relationship): lethargy, stomatitis, diarrhea, dizziness, edema, febrile neutropenia/neutropenic infection occurred at rates ≥10% higher in patients who were 65 years of age or older compared to younger patients. Elderly patients treated with TCF should be closely monitored.

Head and Neck Cancer

Among the 174 and 251 patients who received the induction treatment with docetaxel in combination with cisplatin and fluorouracil (TPF) for SCCHN in the TAX323 and TAX324 studies, 18 (10%) and 32 (13%) of the patients were 65 years of age or older, respectively.

These clinical studies of docetaxel in combination with cisplatin and fluorouracil in patients with SCCHN did not include sufficient numbers of patients aged 65 and over to determine whether they respond differently from younger patients. Other reported clinical experience with this treatment regimen has not identified differences in responses between elderly and younger patients.

8.6 Hepatic Impairment

Avoid docetaxel in patients with bilirubin >ULN and patients with AST and/or ALT >1.5 × ULN concomitant with alkaline phosphatase >2.5 × ULN [see Boxed Warning, Warnings and Precautions (5.2), Clinical Pharmacology (12.3)] .

The alcohol content of Docetaxel injection should be taken into account when given to patients with hepatic impairment [see Warnings and Precautions (5.13)] .

10 OVERDOSAGE

There is no known antidote for docetaxel overdosage. In case of overdosage, the patient should be kept in a specialized unit where vital functions can be closely monitored. Anticipated complications of overdosage include: bone marrow suppression, peripheral neurotoxicity, and mucositis. Patients should receive therapeutic G-CSF as soon as possible after discovery of overdose. Other appropriate symptomatic measures should be taken, as needed.

In two reports of overdose, one patient received 150 mg/m^2and the other received 200 mg/m^2as 1-hour infusions. Both patients experienced severe neutropenia, mild asthenia, cutaneous reactions, and mild paresthesia, and recovered without incident.

In mice, lethality was observed following single intravenous doses that were ≥154 mg/kg (about 4.5 times the human dose of 100 mg/m^2on a mg/m^2basis); neurotoxicity associated with paralysis, non-extension of hind limbs, and myelin degeneration was observed in mice at 48 mg/kg (about 1.5 times the human dose of 100 mg/m^2basis). In male and female rats, lethality was observed at a dose of 20 mg/kg (comparable to the human dose of 100 mg/m^2on a mg/m^2basis) and was associated with abnormal mitosis and necrosis of multiple organs.

11 DESCRIPTION

Docetaxel is an antineoplastic agent belonging to the taxoid family. It is prepared by semisynthesis beginning with a precursor extracted from the renewable needle biomass of yew plants. The chemical name for docetaxel is (2R,3S)-N-carboxy-3-phenylisoserine,N- tert-butyl ester, 13-ester with 5β-20-epoxy-1,2α,4,7β,10β,13α-hexahydroxytax-11-en-9-one 4-acetate 2-benzoate, trihydrate. Docetaxel has the following structural formula:

Docetaxel is a white to almost-white powder with an empirical formula of C43H53NO14∙3H2O, and a molecular weight of 861.9. It is highly lipophilic and practically insoluble in water.

One-vial Docetaxel (Injection)

Docetaxel injection is a sterile, non-pyrogenic, pale-yellow to brownish-yellow solution at 20 mg/mL concentration.

Each mL contains 20 mg docetaxel (anhydrous) in 0.54 grams polysorbate 80 and 0.395 grams dehydrated alcohol (50% v/v) solution, with citric acid for pH adjustment.

Docetaxel is available in single-dose vials containing 20 mg (1 mL), 80 mg (4 mL), or 160 mg (8 mL) docetaxel (anhydrous).

Docetaxel injection requires NO prior dilution with a diluent and is ready to add to the infusion solution.

12 CLINICAL PHARMACOLOGY

12.1 Mechanism of Action

Docetaxel is an antineoplastic agent that acts by disrupting the microtubular network in cells that is essential for mitotic and interphase cellular functions. Docetaxel binds to free tubulin and promotes the assembly of tubulin into stable microtubules while simultaneously inhibiting their disassembly. This leads to the production of microtubule bundles without normal function and to the stabilization of microtubules, which results in the inhibition of mitosis in cells. Docetaxel's binding to microtubules does not alter the number of protofilaments in the bound microtubules, a feature which differs from most spindle poisons currently in clinical use.

12.3 Pharmacokinetics

Absorption

The pharmacokinetics of docetaxel has been evaluated in cancer patients after administration of 20 mg/m^2to 115 mg/m^2in phase 1 studies. The area under the curve (AUC) was dose proportional following doses of 70 mg/m^2to 115 mg/m^2with infusion times of 1 to 2 hours. Docetaxel's pharmacokinetic profile is consistent with a three-compartment pharmacokinetic model, with initial rapid distribution phase and the late (terminal) phase.

Distribution

Mean steady state volume of distribution was 113 L. Docetaxel is approximately 94% protein bound in vitro, mainly to α1-acid glycoprotein, albumin, and lipoproteins. In three cancer patients, the in vitrobinding to plasma proteins was approximately 97%. Dexamethasone does not affect the protein binding of docetaxel.

Elimination

With extended plasma sampling up to 8 to 22 days post infusion, the estimated mean total body clearance was 18 L/h/m^2(range of means: 14 to 23) and mean terminal elimination half-life was 116 hours (range of means: 92 to 135).

Metabolism

Docetaxel is metabolized by the CYP3A4 isoenzyme in vitro [see Drug Interactions (7)] .

Excretion

In three cancer patients urinary and fecal excretion accounted for approximately 6% and 75% of the administered radioactivity, respectively, within 7 days. About 80% of the radioactivity recovered in feces was excreted during the first 48 hours as 1 major and 3 minor metabolites with less than 8% as unchanged drug.

Specific Populations

Effect of Age: A population pharmacokinetic analysis was carried out after docetaxel treatment of 535 patients dosed at 100 mg/m^2. Pharmacokinetic parameters estimated by this analysis were very close to those estimated from phase 1 studies. The pharmacokinetics of docetaxel was not influenced by age.

Effect of Gender: The population pharmacokinetics analysis described above also indicated that gender did not influence the pharmacokinetics of docetaxel.

Hepatic Impairment: The population pharmacokinetic analysis described above indicated that in patients with clinical chemistry data suggestive of mild to moderate liver impairment (AST and/or ALT >1.5 times ULN concomitant with alkaline phosphatase >2.5 times ULN), total body clearance was lowered by an average of 27%, resulting in a 38% increase in systemic exposure (AUC). This average, however, includes a substantial range and there is, at present, no measurement that would allow recommendation for dose adjustment in such patients. Patients with combined abnormalities of transaminase and alkaline phosphatase should not be treated with docetaxel. Patients with severe hepatic impairment have not been studied [see Warnings and Precautions (5.2), Use in Specific Populations (8.6)] .

Effect of Race: Mean total body clearance for Japanese patients dosed at the range of 10 mg/m^2to 90 mg/m^2was similar to that of European/American populations dosed at 100 mg/m^2, suggesting no significant difference in the elimination of docetaxel in the two populations.

Drug Interaction Studies

Effect of Ketoconazole: The effect of ketoconazole (a strong CYP3A4 inhibitor) on the pharmacokinetics of docetaxel was investigated in 7 cancer patients. Patients were randomized to receive either docetaxel (100 mg/m^2intravenous) alone or docetaxel (10 mg/m^2intravenous) in combination with ketoconazole (200 mg orally once daily for 3 days) in a crossover design with a 3-week washout period. The results of this study indicated that the mean dose-normalized AUC of docetaxel was increased 2.2-fold and its clearance was reduced by 49% when docetaxel was coadministered with ketoconazole [see Dosage and Administration (2.7), Drug Interactions (7)] .

Effect of combination therapies

- Dexamethasone: Docetaxel total body clearance was not modified by pretreatment with dexamethasone.
- Cisplatin: Clearance of docetaxel in combination therapy with cisplatin was similar to that previously observed following monotherapy with docetaxel. The pharmacokinetic profile of cisplatin in combination therapy with docetaxel was similar to that observed with cisplatin alone.
- Cisplatin and Fluorouracil: The combined administration of docetaxel, cisplatin and fluorouracil in 12 patients with solid tumors had no influence on the pharmacokinetics of each individual drug.
- Prednisone: A population pharmacokinetic analysis of plasma data from 40 patients with metastatic castration-resistant prostate cancer indicated that docetaxel systemic clearance in combination with prednisone is similar to that observed following administration of docetaxel alone.
- Cyclophosphamide and Doxorubicin: A study was conducted in 30 patients with advanced breast cancer to determine the potential for drug-drug interactions between docetaxel (75 mg/m^2), doxorubicin (50 mg/m^2), and cyclophosphamide (500 mg/m^2) when administered in combination. The coadministration of docetaxel had no effect on the pharmacokinetics of doxorubicin and cyclophosphamide when the three drugs were given in combination compared to coadministration of doxorubicin and cyclophosphamide only. In addition, doxorubicin and cyclophosphamide had no effect on docetaxel plasma clearance when the three drugs were given in combination compared to historical data for docetaxel monotherapy.

13 NONCLINICAL TOXICOLOGY

13.1 Carcinogenesis, Mutagenesis, Impairment of Fertility

Carcinogenicity studies with docetaxel have not been performed.

Docetaxel was genotoxic by an aneugenic mechanism in the in vitrochromosome aberration test in CHO-K1cells and in the in vivomicronucleus test in mice administered doses of 0.39 to 1.56 mg/kg (about 1/60thto 1/15ththe recommended human dose on a mg/m^2basis). Docetaxel was not mutagenic in the Ames test or the CHO/HGPRT gene mutation assays.

Docetaxel did not reduce fertility in rats when administered in multiple intravenous doses of up to 0.3 mg/kg (about 1/50ththe recommended human dose on a mg/m^2basis), but decreased testicular weights were reported. This correlates with findings of a 10-cycle toxicity study (dosing once every 21 days for 6 months) in rats and dogs in which testicular atrophy or degeneration was observed at intravenous doses of 5 mg/kg in rats and 0.375 mg/kg in dogs (about 1/3rdand 1/15ththe recommended human dose on a mg/m^2basis, respectively). An increased frequency of dosing in rats produced similar effects at lower dose levels.

14 CLINICAL STUDIES

14.1 Locally Advanced or Metastatic Breast Cancer

The efficacy and safety of docetaxel have been evaluated in locally advanced or metastatic breast cancer after failure of previous chemotherapy (alkylating agent-containing regimens or anthracycline-containing regimens).

Randomized Trials

In one randomized trial, patients with a history of prior treatment with an anthracycline-containing regimen were assigned to treatment with docetaxel (100 mg/m^2every 3 weeks) or the combination of mitomycin (12 mg/m^2every 6 weeks) and vinblastine (6 mg/m^2every 3 weeks). Two hundred three patients were randomized to docetaxel and 189 to the comparator arm. Most patients had received prior chemotherapy for metastatic disease; only 27 patients on the docetaxel arm and 33 patients on the comparator arm entered the study following relapse after adjuvant therapy. Three-quarters of patients had measurable, visceral metastases. The primary endpoint was time to progression. The following table summarizes the study results. (See Table 12.)

Table 12: Efficacy of Docetaxel in the Treatment of Breast Cancer Patients Previously Treated with an Anthracycline-Containing Regimen (Intent-to-Treat Analysis)
Efficacy Parameter | Docetaxel (n=203) | Mitomycin/Vinblastine (n=189) | p-value
Median Survival | 11.4 months | 8.7 months
Risk Ratio [For the risk ratio, a value less than 1.00 favors docetaxel.] , Mortality (Docetaxel: Control) | 0.73 |  | p=0.01 Log Rank
95% CI (Risk Ratio) | 0.58–0.93
Median Time to Progression | 4.3 months | 2.5 months
Risk Ratio , Progression (Docetaxel: Control) | 0.75 |  | p=0.01 Log Rank
95% CI (Risk Ratio) | 0.61–0.94
Overall Response Rate | 28.1% | 9.5% | p<0.0001
Complete Response Rate | 3.4% | 1.6% | Chi Square

In a second randomized trial, patients previously treated with an alkylating-containing regimen were assigned to treatment with docetaxel (100 mg/m^2) or doxorubicin (75 mg/m^2) every 3 weeks. One hundred sixty-one patients were randomized to docetaxel and 165 patients to doxorubicin. Approximately one-half of patients had received prior chemotherapy for metastatic disease, and one-half entered the study following relapse after adjuvant therapy. Three-quarters of patients had measurable, visceral metastases. The primary endpoint was time to progression. The study results are summarized below. (See Table 13.)

Table 13: Efficacy of Docetaxel in the Treatment of Breast Cancer Patients Previously Treated with an Alkylating-Containing Regimen (Intent-to-Treat Analysis)
Efficacy Parameter | Docetaxel (n=161) | Doxorubicin (n=165) | p-value
Median Survival | 14.7 months | 14.3 months
Risk Ratio [For the risk ratio, a value less than 1.00 favors docetaxel.] , Mortality (Docetaxel: Control) | 0.89 |  | p=0.39 Log Rank
95% CI (Risk Ratio) | 0.68–1.16
Median Time to Progression | 6.5 months | 5.3 months
Risk Ratio , Progression (Docetaxel: Control) | 0.93 |  | p=0.45 Log Rank
95% CI (Risk Ratio) | 0.71–1.16
Overall Response Rate | 45.3% | 29.7% | p=0.004
Complete Response Rate | 6.8% | 4.2% | Chi Square

In another multicenter open-label, randomized trial (TAX313), in the treatment of patients with advanced breast cancer who progressed or relapsed after one prior chemotherapy regimen, 527 patients were randomized to receive docetaxel monotherapy 60 mg/m^2(n=151), 75 mg/m^2(n=188) or 100 mg/m^2(n=188). In this trial, 94% of patients had metastatic disease and 79% had received prior anthracycline therapy. Response rate was the primary endpoint. Response rates increased with docetaxel dose: 19.9% for the 60 mg/m^2group compared to 22.3% for the 75 mg/m^2and 29.8% for the 100 mg/m^2group; pair-wise comparison between the 60 mg/m^2and 100 mg/m^2groups was statistically significant (p=0.037).

Single Arm Studies

Docetaxel at a dose of 100 mg/m^2was studied in six single arm studies involving a total of 309 patients with metastatic breast cancer in whom previous chemotherapy had failed. Among these, 190 patients had anthracycline-resistant breast cancer, defined as progression during an anthracycline-containing chemotherapy regimen for metastatic disease, or relapse during an anthracycline-containing adjuvant regimen. In anthracycline-resistant patients, the overall response rate was 37.9% (72/190; 95% CI: 31.0–44.8) and the complete response rate was 2.1%.

Docetaxel was also studied in three single arm Japanese studies at a dose of 60 mg/m^2, in 174 patients who had received prior chemotherapy for locally advanced or metastatic breast cancer. Among 26 patients whose best response to an anthracycline had been progression, the response rate was 34.6% (95% CI: 17.2–55.7), similar to the response rate in single arm studies of 100 mg/m^2.

14.2 Adjuvant Treatment of Breast Cancer

A multicenter, open-label, randomized trial (TAX316) evaluated the efficacy and safety of docetaxel for the adjuvant treatment of patients with axillary-node-positive breast cancer and no evidence of distant metastatic disease. After stratification according to the number of positive lymph nodes (1–3, 4+), 1491 patients were randomized to receive either docetaxel 75 mg/m^2administered 1-hour after doxorubicin 50 mg/m^2and cyclophosphamide 500 mg/m^2(TAC arm), or doxorubicin 50 mg/m^2followed by fluorouracil 500 mg/m^2and cyclophosphamide 500 mg/m^2(FAC arm). Both regimens were administered every 3 weeks for 6 cycles. Docetaxel was administered as a 1-hour infusion; all other drugs were given as intravenous bolus on day 1. In both arms, after the last cycle of chemotherapy, patients with positive estrogen and/or progesterone receptors received tamoxifen 20 mg daily for up to 5 years. Adjuvant radiation therapy was prescribed according to guidelines in place at participating institutions and was given to 69% of patients who received TAC and 72% of patients who received FAC.

Results from a second interim analysis (median follow-up 55 months) are as follows: In study TAX316, the docetaxel-containing combination regimen TAC showed significantly longer disease-free survival (DFS) than FAC (hazard ratio=0.74; 2-sided 95% CI=0.60, 0.92, stratified log rank p=0.0047). The primary endpoint, disease-free survival, included local and distant recurrences, contralateral breast cancer and deaths from any cause. The overall reduction in risk of relapse was 25.7% for TAC-treated patients. (See Figure 1.)

At the time of this interim analysis, based on 219 deaths, overall survival was longer for TAC than FAC (hazard ratio=0.69, 2-sided 95% CI=0.53, 0.90). (See Figure 2.) There will be further analysis at the time survival data mature.

Figure 1: TAX316 Disease Free Survival K-M curve

Figure 2: TAX316 Overall Survival K-M Curve

The following table describes the results of subgroup analyses for DFS and OS (see Table 14).

Table 14: Subset Analyses-Adjuvant Breast Cancer Study
 |  | Disease Free Survival |  | Overall Survival
Patient subset | Number of patients | Hazard ratio [a hazard ratio of less than 1 indicates that TAC is associated with a longer disease free survival or overall survival compared to FAC.] | 95% CI | Hazard ratio | 95% CI
No. of positive nodes
Overall | 744 | 0.74 | (0.60, 0.92) | 0.69 | (0.53, 0.90)
1–3 | 467 | 0.64 | (0.47, 0.87) | 0.45 | (0.29, 0.70)
4+ | 277 | 0.84 | (0.63, 1.12) | 0.93 | (0.66, 1.32)
Receptor status
Positive | 566 | 0.76 | (0.59, 0.98) | 0.69 | (0.48, 0.99)
Negative | 178 | 0.68 | (0.48, 0.97) | 0.66 | (0.44, 0.98)

14.3 Non-small Cell Lung Cancer (NSCLC)

The efficacy and safety of docetaxel has been evaluated in patients with unresectable, locally advanced or metastatic non-small cell lung cancer whose disease has failed prior platinum-based chemotherapy or in patients who are chemotherapy naive.

Monotherapy with Docetaxel for NSCLC Previously Treated with Platinum-Based Chemotherapy

Two randomized, controlled trials established that a docetaxel dose of 75 mg/m^2was tolerable and yielded a favorable outcome in patients previously treated with platinum-based chemotherapy (see below). Docetaxel at a dose of 100 mg/m^2, however, was associated with unacceptable hematologic toxicity, infections, and treatment-related mortality and this dose should not be used [see Boxed Warning, Dosage and Administration (2.7), Warnings and Precautions (5.3)] .

One trial (TAX317), randomized patients with locally advanced or metastatic non-small cell lung cancer, a history of prior platinum-based chemotherapy, no history of taxane exposure, and an ECOG performance status ≤2 to docetaxel or best supportive care. The primary endpoint of the study was survival. Patients were initially randomized to docetaxel 100 mg/m^2or best supportive care, but early toxic deaths at this dose led to a dose reduction to docetaxel 75 mg/m^2. A total of 104 patients were randomized in this amended study to either docetaxel 75 mg/m^2or best supportive care.

In a second randomized trial (TAX320), 373 patients with locally advanced or metastatic non-small cell lung cancer, a history of prior platinum-based chemotherapy, and an ECOG performance status ≤2 were randomized to docetaxel 75 mg/m^2, docetaxel 100 mg/m^2and a treatment in which the investigator chose either vinorelbine 30 mg/m^2days 1, 8, and 15 repeated every 3 weeks or ifosfamide 2 g/m^2days 1–3 repeated every 3 weeks. Forty percent of the patients in this study had a history of prior paclitaxel exposure. The primary endpoint was survival in both trials. The efficacy data for the docetaxel 75 mg/m^2arm and the comparator arms are summarized in Table 15and Figures 3and 4showing the survival curves for the two studies.

Table 15: Efficacy of Docetaxel in the Treatment of Non-small Cell Lung Cancer Patients Previously Treated with a Platinum-Based Chemotherapy Regimen (Intent-to-Treat Analysis)
 | TAX317 |  | TAX320
 | Docetaxel 75 mg/m^2 n=55 | Best Supportive Care n=49 | Docetaxel 75 mg/m^2 n=125 | Control (V/I [Vinorelbine/Ifosfamide]) n=123
Overall Survival Log-rank Test | p=0.01 |  | p=0.13
Risk Ratio [a value less than 1.00 favors docetaxel] , Mortality (Docetaxel: Control) 95% CI (Risk Ratio) | 0.56 (0.35, 0.88) |  | 0.82 (0.63, 1.06)
Median Survival 95% CI | 7.5 months [p≤0.05] (5.5, 12.8) | 4.6 months (3.7, 6.1) | 5.7 months (5.1, 7.1) | 5.6 months (4.4, 7.9)
% 1-year Survival 95% CI | 37% [uncorrected for multiple comparisons] (24, 50) | 12% (2, 23) | 30% (22, 39) | 20% (13, 27)
Time to Progression 95% CI | 12.3 weeks (9.0, 18.3) | 7.0 weeks (6.0, 9.3) | 8.3 weeks (7.0, 11.7) | 7.6 weeks (6.7, 10.1)
Response Rate | 5.5% | Not Applicable | 5.7% | 0.8%
95% CI | (1.1, 15.1) |  | (2.3, 11.3) | (0.0, 4.5)

Only one of the two trials (TAX317) showed a clear effect on survival, the primary endpoint; that trial also showed an increased rate of survival to one year. In the second study (TAX320) the rate of survival at one year favored docetaxel 75 mg/m^2.

Figure 3: TAX317 Survival K-M Curves - Docetaxel 75 mg/m^2Versus Best Supportive Care

Figure 4: TAX320 Survival K-M Curves - Docetaxel 75 mg/m^2Versus Vinorelbine or Ifosfamide Control

Patients treated with docetaxel at a dose of 75 mg/m^2experienced no deterioration in performance status and body weight relative to the comparator arms used in these trials.

Combination Therapy with Docetaxel for Chemotherapy-Naive NSCLC

In a randomized controlled trial (TAX326), 1218 patients with unresectable stage IIIB or IV NSCLC and no prior chemotherapy were randomized to receive one of three treatments: docetaxel 75 mg/m^2as a 1 hour infusion immediately followed by cisplatin 75 mg/m^2over 30 to 60 minutes every 3 weeks; vinorelbine 25 mg/m^2administered over 6–10 minutes on days 1, 8, 15, 22 followed by cisplatin 100 mg/m^2administered on day 1 of cycles repeated every 4 weeks; or a combination of docetaxel and carboplatin.

The primary efficacy endpoint was overall survival. Treatment with docetaxel+cisplatin did not result in a statistically significantly superior survival compared to vinorelbine+cisplatin (see table below). The 95% confidence interval of the hazard ratio (adjusted for interim analysis and multiple comparisons) shows that the addition of docetaxel to cisplatin results in an outcome ranging from a 6% inferior to a 26% superior survival compared to the addition of vinorelbine to cisplatin. The results of a further statistical analysis showed that at least (the lower bound of the 95% confidence interval) 62% of the known survival effect of vinorelbine when added to cisplatin (about a 2-month increase in median survival; Wozniak et al. JCO, 1998) was maintained. The efficacy data for the docetaxel+cisplatin arm and the comparator arm are summarized in Table 16.

Table 16: Survival Analysis of Docetaxel in Combination Therapy for Chemotherapy-Naive NSCLC
Comparison | Docetaxel + Cisplatin n=408 | Vinorelbine + Cisplatin n=405
Kaplan-Meier Estimate of Median Survival | 10.9 months | 10.0 months
p-value [From the superiority test (stratified log rank) comparing docetaxel+cisplatin to vinorelbine+cisplatin] | 0.122
Estimated Hazard Ratio [Hazard ratio of docetaxel+cisplatin versus vinorelbine+cisplatin. A hazard ratio of less than 1 indicates that docetaxel+cisplatin is associated with a longer survival.] | 0.88
Adjusted 95% CI [Adjusted for interim analysis and multiple comparisons.] | (0.74, 1.06)

The second comparison in the same three-arm study, vinorelbine+cisplatin versus docetaxel+carboplatin, did not demonstrate superior survival associated with the docetaxel arm (Kaplan-Meier estimate of median survival was 9.1 months for docetaxel+carboplatin compared to 10.0 months on the vinorelbine+cisplatin arm) and the docetaxel+carboplatin arm did not demonstrate preservation of at least 50% of the survival effect of vinorelbine added to cisplatin. Secondary endpoints evaluated in the trial included objective response and time to progression. There was no statistically significant difference between docetaxel+cisplatin and vinorelbine+cisplatin with respect to objective response and time to progression (see Table 17).

Table 17: Response and TTP Analysis of Docetaxel in Combination Therapy for Chemotherapy-Naive NSCLC
Endpoint | Docetaxel + Cisplatin | Vinorelbine + Cisplatin | p-value
Objective Response Rate (95% CI) [Adjusted for multiple comparisons.] | 31.6% (26.5%, 36.8%) | 24.4% (19.8%, 29.2%) | Not Significant
Median Time to Progression [Kaplan-Meier estimates.] (95% CI) | 21.4 weeks (19.3, 24.6) | 22.1 weeks (18.1, 25.6) | Not Significant

14.4 Castration-Resistant Prostate Cancer

The safety and efficacy of docetaxel in combination with prednisone in patients with metastatic castration-resistant prostate cancer were evaluated in a randomized multicenter active control trial. A total of 1006 patients with Karnofsky Performance Status (KPS) ≥60 were randomized to the following treatment groups:

- Docetaxel 75 mg/m^2every 3 weeks for 10 cycles.
- Docetaxel 30 mg/m^2administered weekly for the first 5 weeks in a 6-week cycle for 5 cycles.
- Mitoxantrone 12 mg/m^2every 3 weeks for 10 cycles.

All 3 regimens were administered in combination with prednisone 5 mg twice daily, continuously.

In the docetaxel every three week arm, a statistically significant overall survival advantage was demonstrated compared to mitoxantrone. In the docetaxel weekly arm, no overall survival advantage was demonstrated compared to the mitoxantrone control arm. Efficacy results for the docetaxel every 3 week arm versus the control arm are summarized in Table 18and Figure 5.

Table 18: Efficacy of Docetaxel in the Treatment of Patients with Metastatic Castration-Resistant Prostate Cancer (Intent-to-Treat Analysis)
 | Docetaxel + Prednisone every 3 weeks | Mitoxantrone + Prednisone every 3 weeks
Number of patients | 335 | 337
Median survival (months) | 18.9 | 16.5
95% CI | (17.0–21.2) | (14.4–18.6)
Hazard ratio | 0.761 | --
95% CI | (0.619–0.936) | --
p-value [Stratified log-rank test. Threshold for statistical significance = 0.0175 because of 3 arms.] | 0.0094 | --

Figure 5: TAX327 Survival K-M Curves

14.5 Gastric Adenocarcinoma

A multicenter, open-label, randomized trial was conducted to evaluate the safety and efficacy of docetaxel for the treatment of patients with advanced gastric adenocarcinoma, including adenocarcinoma of the gastroesophageal junction, who had not received prior chemotherapy for advanced disease. A total of 445 patients with KPS >70 were treated with either docetaxel (T) (75 mg/m^2on day 1) in combination with cisplatin (C) (75 mg/m^2on day 1) and fluorouracil (F) (750 mg/m^2per day for 5 days) or cisplatin (100 mg/m^2on day 1) and fluorouracil (1000 mg/m^2per day for 5 days). The length of a treatment cycle was 3 weeks for the TCF arm and 4 weeks for the CF arm. The demographic characteristics were balanced between the two treatment arms. The median age was 55 years, 71% were male, 71% were Caucasian, 24% were 65 years of age or older, 19% had a prior curative surgery and 12% had palliative surgery. The median number of cycles administered per patient was 6 (with a range of 1–16) for the TCF arm compared to 4 (with a range of 1–12) for the CF arm. Time to progression (TTP) was the primary endpoint and was defined as time from randomization to disease progression or death from any cause within 12 weeks of the last evaluable tumor assessment or within 12 weeks of the first infusion of study drugs for patients with no evaluable tumor assessment after randomization. The hazard ratio (HR) for TTP was 1.47 (CF/TCF, 95% CI: 1.19–1.83) with a significantly longer TTP (p=0.0004) in the TCF arm. Approximately 75% of patients had died at the time of this analysis. Overall survival was significantly longer (p=0.0201) in the TCF arm with a HR of 1.29 (95% CI: 1.04–1.61). Efficacy results are summarized in Table 19and Figures 6and 7.

Table 19: Efficacy of Docetaxel in the Treatment of Patients with Gastric Adenocarcinoma
Endpoint | TCF n=221 | CF n=224
Median TTP (months) (95% CI) | 5.6 (4.86–5.91) | 3.7 (3.45–4.47)
Hazard ratio [For the hazard ratio (TCF/CF), values less than 1.00 favor the docetaxel arm.] (95% CI) [Unstratified log-rank test] p-value | 0.68 (0.55–0.84) 0.0004
Median survival (months) (95% CI) | 9.2 (8.38–10.58) | 8.6 (7.16–9.46)
Hazard ratio (95% CI) p-value | 0.77 (0.62–0.96) 0.0201
Overall Response Rate (CR+PR) (%) | 36.7 | 25.4
p-value | 0.0106

Subgroup analyses were consistent with the overall results across age, gender and race.

Figure 6: Gastric Cancer Study (TAX325) Time to Progression K-M Curve

Figure 7: Gastric Cancer Study (TAX325) Survival K-M Curve

14.6 Head and Neck Cancer

Induction Chemotherapy Followed by Radiotherapy (TAX323)

The safety and efficacy of docetaxel in the induction treatment of patients with squamous cell carcinoma of the head and neck (SCCHN) was evaluated in a multicenter, open-label, randomized trial (TAX323). In this study, 358 patients with inoperable locally advanced SCCHN, and WHO performance status 0 or 1, were randomized to one of two treatment arms. Patients on the docetaxel arm received docetaxel (T) 75 mg/m^2followed by cisplatin (P) 75 mg/m^2on Day 1, followed by fluorouracil (F) 750 mg/m^2per day as a continuous infusion on Days 1–5. The cycles were repeated every three weeks for 4 cycles. Patients whose disease did not progress received radiotherapy (RT) according to institutional guidelines (TPF/RT). Patients on the comparator arm received cisplatin (P) 100 mg/m^2on Day 1, followed by fluorouracil (F) 1000 mg/m^2/day as a continuous infusion on Days 1–5. The cycles were repeated every three weeks for 4 cycles. Patients whose disease did not progress received RT according to institutional guidelines (PF/RT). At the end of chemotherapy, with a minimal interval of 4 weeks and a maximal interval of 7 weeks, patients whose disease did not progress received radiotherapy (RT) according to institutional guidelines. Locoregional therapy with radiation was delivered either with a conventional fraction regimen (1.8 Gy–2.0 Gy once a day, 5 days per week for a total dose of 66 to 70 Gy) or with an accelerated/hyperfractionated regimen (twice a day, with a minimum interfraction interval of 6 hours, 5 days per week, for a total dose of 70 to 74 Gy, respectively). Surgical resection was allowed following chemotherapy, before or after radiotherapy.

The primary endpoint in this study, progression-free survival (PFS), was significantly longer in the TPF arm compared to the PF arm, p=0.0077 (median PFS: 11.4 vs 8.3 months, respectively) with an overall median follow-up time of 33.7 months. Median overall survival with a median follow-up of 51.2 months was also significantly longer in favor of the TPF arm compared to the PF arm (median OS: 18.6 vs 14.2 months, respectively). Efficacy results are presented in Table 20and Figures 8and 9.

Table 20: Efficacy of Docetaxel in the Induction Treatment of Patients with Inoperable Locally Advanced SCCHN (Intent-to-Treat Analysis)
Endpoint | Docetaxel + Cisplatin + Fluorouracil n=177 | Cisplatin + Fluorouracil n=181
Median progression free survival (months) (95% CI) | 11.4 (10.1–14.0) | 8.3 (7.4–9.1)
Adjusted Hazard ratio (95% CI) [Stratified log-rank test based on primary tumor site] p-value | 0.71 (0.56–0.91) 0.0077
Median survival (months) (95% CI) | 18.6 (15.7–24.0) | 14.2 (11.5–18.7)
Hazard ratio (95% CI) [Stratified log-rank test, not adjusted for multiple comparisons] p-value | 0.71 (0.56–0.90) 0.0055
Best overall response (CR + PR) to chemotherapy (%) (95% CI) | 67.8 (60.4–74.6) | 53.6 (46.0–61.0)
[Chi square test, not adjusted for multiple comparisons] p-value | 0.006
Best overall response (CR + PR) to study treatment [chemotherapy +/- radiotherapy] (%) (95% CI) | 72.3 (65.1–78.8) | 58.6 (51.0–65.8)
p-value | 0.006
A Hazard ratio of less than 1 favors docetaxel+cisplatin+fluorouracil

Figure 8: TAX323 Progression-Free Survival K-M Curve

Figure 9: TAX323 Overall Survival K-M Curve

Induction Chemotherapy Followed by Chemoradiotherapy (TAX324)

The safety and efficacy of docetaxel in the induction treatment of patients with locally advanced (unresectable, low surgical cure, or organ preservation) SCCHN was evaluated in a randomized, multicenter open-label trial (TAX324). In this study, 501 patients, with locally advanced SCCHN, and a WHO performance status of 0 or 1, were randomized to one of two treatment arms. Patients on the docetaxel arm received docetaxel (T) 75 mg/m^2by intravenous infusion on day 1 followed by cisplatin (P) 100 mg/m^2administered as a 30-minute to three-hour intravenous infusion, followed by the continuous intravenous infusion of fluorouracil (F) 1000 mg/m^2/day from day 1 to day 4. The cycles were repeated every 3 weeks for 3 cycles. Patients on the comparator arm received cisplatin (P) 100 mg/m^2as a 30-minute to three-hour intravenous infusion on day 1 followed by the continuous intravenous infusion of fluorouracil (F) 1000 mg/m^2/day from day 1 to day 5. The cycles were repeated every 3 weeks for 3 cycles.

All patients in both treatment arms who did not have progressive disease were to receive 7 weeks of chemoradiotherapy (CRT) following induction chemotherapy 3 to 8 weeks after the start of the last cycle. During radiotherapy, carboplatin (AUC 1.5) was given weekly as a one-hour intravenous infusion for a maximum of 7 doses. Radiation was delivered with megavoltage equipment using once daily fractionation (2 Gy per day, 5 days per week for 7 weeks for a total dose of 70–72 Gy). Surgery on the primary site of disease and/or neck could be considered at any time following completion of CRT.

The primary efficacy endpoint, overall survival (OS), was significantly longer (log-rank test, p=0.0058) with the docetaxel-containing regimen compared to PF (median OS: 70.6 vs 30.1 months, respectively, hazard ratio [HR]=0.70, 95% confidence interval [CI]=0.54–0.90). Overall survival results are presented in Table 21and Figure 10.

Table 21: Efficacy of Docetaxel in the Induction Treatment of Patients with Locally Advanced SCCHN (Intent-to-Treat Analysis)
Endpoint | Docetaxel + Cisplatin + Fluorouracil n=255 | Cisplatin + Fluorouracil n=246
Median overall survival (months) (95% CI) | 70.6 (49.0–NE) | 30.1 (20.9–51.5)
Hazard ratio: (95% CI) [unadjusted log-rank test] p-value | 0.70 (0.54–0.90) 0.0058
A Hazard ratio of less than 1 favors docetaxel+cisplatin+fluorouracil
NE - not estimable

Figure 10: TAX324 Overall Survival K-M Curve

15 REFERENCES

1. "OSHA Hazardous Drugs." http://www.osha.gov/SLTC/hazardousdrugs/index.html

16 HOW SUPPLIED/STORAGE AND HANDLING

16.1 How Supplied

One-vial Docetaxel (Injection)

Docetaxel injection is supplied in a single-dose vial as a sterile, pyrogen-free, non-aqueous solution. Discard unused portion.

Docetaxel 20 mg/mL | (NDC 0955-1020-01)

Docetaxel injection 20 mg/1 mL: 20 mg docetaxel in 1 mL 50/50 (v/v) ratio polysorbate 80/dehydrated alcohol.

The vial is in a blister pack in one carton.

Docetaxel 80 mg/4 mL | (NDC 0955-1021-04)

Docetaxel injection 80 mg/4 mL: 80 mg docetaxel in 4 mL 50/50 (v/v) ratio polysorbate 80/dehydrated alcohol.

The vial is in a blister pack in one carton.

Docetaxel 160 mg/8 mL | (NDC 0955-1022-08)

Docetaxel injection 160 mg/8 mL: 160 mg docetaxel in 8 mL 50/50 (v/v) ratio polysorbate 80/dehydrated alcohol.

The vial is in a blister pack in one carton.

16.2 Storage

Store between 2°C and 25°C (36°F and 77°F). Retain in the original package to protect from light. Freezing does not adversely affect the product.

16.3 Handling and Disposal

Docetaxel is a hazardous drug. Follow applicable special handling and disposal procedures.

17 PATIENT COUNSELING INFORMATION

Advise the patient to read the FDA-approved patient labeling (Patient Information).

Bone Marrow Suppression

Advise patients that periodic assessment of their blood count will be performed to detect neutropenia, thrombocytopenia, and/or anemia [see Contraindications (4), Warnings and Precautions (5.3)] . Instruct patients to monitor their temperature frequently and immediately report any occurrence of fever.

Enterocolitis and Neutropenic Colitis

Advise patients of the symptoms of colitis, such as abdominal pain or tenderness, and/or diarrhea, with or without fever, and instruct patients to promptly contact their healthcare provider if they experience these symptoms [see Dosage and Administration (2.7)and Warnings and Precautions (5.4)] .

Hypersensitivity Reactions

Ask patients whether they have previously received paclitaxel therapy, and if they have experienced a hypersensitivity reaction to paclitaxel. Instruct patients to immediately report to their healthcare provider signs of a hypersensitivity reaction [see Contraindications (4), Warnings and Precautions (5.5)] .

Fluid Retention

Advise patients to report signs of fluid retention such as peripheral edema in the lower extremities, weight gain, and dyspnea immediately to their healthcare provider [see Warnings and Precautions (5.6)] .

Second Primary Malignancies

Advise patients on the risk of second primary malignancies during treatment with docetaxel [see Warnings and Precautions (5.7)] .

Cutaneous Reactions

Advise patients that localized erythema of the extremities and severe skin toxicities may occur. Instruct patients to immediately report severe cutaneous reactions to their healthcare provider [see Dosage and Administration (2.7)and Warnings and Precautions (5.8)] .

Neurologic Reactions

Advise patients that neurosensory symptoms or peripheral neuropathy may occur. Instruct patients to immediately report neurologic reactions to their healthcare provider [see Dosage and Administration (2.7)and Warnings and Precautions (5.9)] .

Eye Disorders

Advise patients that vision disturbances and excessive tearing are associated with docetaxel administration. Instruct patients to immediately report any vision changes to their healthcare provider [see Warnings and Precautions (5.10)] .

Gastrointestinal Reactions

Explain to patients that nausea, vomiting, diarrhea, and constipation are associated with docetaxel administration. Instruct patients to report any severe events to their healthcare provider [see Adverse Reactions (6)] .

Cardiac Disorders

Advise patients to report any irregular and/or rapid heartbeat, severe shortness of breath, dizziness, and/or fainting immediately to their healthcare provider [see Adverse Reactions (6)] .

Other Common Adverse Reactions

Advise patients that other common adverse reactions associated with docetaxel may include alopecia (cases of permanent hair loss have been reported), asthenia, anorexia, dysgeusia, mucositis, myalgia, nail disorders, or pain. Instruct patients to report these reactions to their healthcare provider if serious events occur [see Adverse Reactions (6)] .

Importance of Corticosteroids

Explain the significance of oral corticosteroids such as dexamethasone administration to the patient to help facilitate compliance. Instruct patients to report to their healthcare provider if they were not compliant with the oral corticosteroid regimen [see Dosage and Administration (2.6)] .

Embryo-Fetal Toxicity

Docetaxel can cause fetal harm. Advise patients to inform their healthcare provider of a known or suspected pregnancy. Advise patients to avoid becoming pregnant while receiving this drug. Advise female patients of reproductive potential to use effective contraceptives during treatment and for 2 months after the last dose of docetaxel. Advise male patients with female partners of reproductive potential to use effective contraception during treatment and for 4 months after the last dose of docetaxel [see Warnings and Precautions (5.12), and Use in Specific Populations (8.1, 8.3)] .

Lactation

Advise women not to breastfeed during docetaxel treatment and for 1 week after the last dose [see Use in Specific Populations (8.2)] .

Infertility

Advise males of reproductive potential that docetaxel may impair fertility [see Nonclinical Toxicology (13.1)] .

Alcohol Content in Docetaxel

Explain to patients the possible effects of the alcohol content in docetaxel, including possible effects on the central nervous system [see Warnings and Precautions (5.13)] .

Tumor Lysis Syndrome

Advise patients of the potential risk of tumor lysis syndrome and to immediately report any signs or symptoms associated with this event (nausea, vomiting, confusion, shortness of breath, seizure, irregular heartbeat, dark or cloudy urine, reduced amount of urine, unusual tiredness, muscle cramps) to their healthcare provider. Advise patients of the importance of keeping scheduled appointment for blood work or other laboratory tests and of drinking adequate fluids to avoid dehydration [see Warnings and Precautions (5.14)] .

Ability to Drive or Operate Machines

Explain to patients that docetaxel may impair their ability to drive or operate machines due to its side effects [see Adverse Reactions (6)] or due to the alcohol content of Docetaxel injection [see Warnings and Precautions (5.13)] . Advise them not to drive or use machines if they experience these side effects during treatment.

Drug Interactions

Inform patients about the risk of drug interactions and the importance of providing a list of prescription and non-prescription drugs to their healthcare provider [see Drug Interactions (7)] .

Winthrop U.S.,
a business of sanofi-aventis U.S. LLC
Bridgewater, NJ 08807
A SANOFI COMPANY
©2023 sanofi-aventis U.S. LLC

Patient Information
Docetaxel (DOSE-ē-tāx-el)
Injection
for intravenous use

What is the most important information I should know about Docetaxel injection?

Docetaxel can cause serious side effects, including death.

- The chance of death in people who receive docetaxel is higher if you:
  - have liver problems
  - receive high doses of docetaxel
  - have non-small cell lung cancer and have been treated with chemotherapy medicines that contain platinum
- Docetaxel can affect your blood cells.Your healthcare provider should do routine blood tests during treatment with docetaxel. This will include regular checks of your white blood cell counts. If your white blood cells are too low, your healthcare provider may not treat you with docetaxel until you have enough white blood cells. People with low white blood cell counts can develop life-threatening infections. The earliest sign of infection may be fever. Follow your healthcare provider's instructions for how often to take your temperature during treatment with docetaxel. Call your healthcare provider right away if you have a fever.
- Swelling (inflammation) of the small intestine and colon.This can happen at any time during treatment and could lead to death as early as the first day you get symptoms. Tell your healthcare provider right away if you develop new or worse symptoms of intestinal problems, including stomach (abdominal) pain or tenderness or diarrhea, with or without fever.
- Severe allergic reactionsare medical emergencies that can happen in people who receive docetaxel and can lead to death. You may be at higher risk of developing a severe allergic reaction to docetaxel if you are allergic to paclitaxel. Your healthcare provider will monitor you closely for allergic reactions during your docetaxel infusion.
  Tell your healthcare provider right away if you have any of these signs of a severe allergic reaction:
  - trouble breathing
  - sudden swelling of your face, lips, tongue, throat, or trouble swallowing
  - hives (raised bumps), rash, or redness all over your body
- Your body may hold too much fluid (severe fluid retention)during treatment with docetaxel. This can be life threatening. To decrease the chance of this happening, you must take another medicine, a corticosteroid, before each docetaxel treatment. You must take the corticosteroid exactly as your healthcare provider tells you. Tell your healthcare provider or nurse before your docetaxel treatment if you forgot to take your corticosteroid dose or do not take it as your healthcare provider tells you. Tell your healthcare provider right away if you have swelling in your legs or feet, weight gain or shortness of breath.
- Risk of new cancers.An increase in new (second) cancers has happened in people treated with Docetaxel together with certain other anticancer treatments. This includes certain blood cancers, such as acute myeloid leukemia (AML), myelodysplastic syndrome (MDS), non-Hodgkin's Lymphoma (NHL), and kidney cancer.
  - Changes in blood counts due to leukemia and other blood disorders may occur years after treatment with docetaxel.
  Your healthcare provider will check you for new cancers during and after your treatment with docetaxel.
- Severe skin problems.
  Tell your healthcare provider right away if you have any of these signs of a severe skin reaction:
  - redness and swelling of your arms and legs.
  - blistering, peeling, or bleeding on any part of your skin (including your lips, eyes, mouth, nose, genitals, hands or feet) with or without a rash. You may also have flu-like symptoms such as fever, chills, or muscle aches.
  - red, scaly rash all over your body with blisters, small red or white bumps under the skin that contain pus (pustules), and fever.

What is Docetaxel injection?

Docetaxel is a prescription anticancer medicine used to treat certain people with:

- breast cancer
- non-small cell lung cancer
- prostate cancer
- stomach cancer
- head and neck cancer

It is not known if docetaxel is effective in children.

Do not receive Docetaxel if you:

- have a low white blood cell count.
- have had a severe allergic reaction to:
  - docetaxel, the active ingredient in Docetaxel injection, or
  - any other medicines that contain polysorbate 80. Ask your healthcare provider or pharmacist if you are not sure.

See " What is the most important information I should know about Docetaxel injection?" for the signs and symptoms of a severe allergic reaction.

See the end of this Patient Information for a complete list of the ingredients in docetaxel.

Before you receive Docetaxel injection, tell your healthcare provider about all of your medical conditions, including if you:

- are allergic to any medicines, including paclitaxel. See " Do not receive docetaxel if you".
- have liver problems
- have kidney problems
- are pregnant or plan to become pregnant. Docetaxel can harm your unborn baby. You should not become pregnant during treatment with docetaxel. Tell your healthcare provider if you become pregnant or you think you may be pregnant during treatment with docetaxel.
  Females who are able to become pregnant:
  - Your healthcare provider will check to see if you are pregnant before you start treatment with docetaxel.
  - You should use effective birth control (contraception) during treatment with docetaxel and for 2 months after the last dose.
  Maleswith female partners who are able to become pregnant should use effective birth control during treatment with docetaxel and for 4 months after the last dose.
  Talk to your healthcare provider if you have questions about birth control options that are right for you.
- are breastfeeding or plan to breastfeed. It is not known if docetaxel passes into your breast milk. Do not breastfeed during treatment with docetaxel and for 1 week after the last dose.

Tell your healthcare provider about all the medicines you take, including prescription and over-the-counter medicines, vitamins, and herbal supplements. Docetaxel may affect the way other medicines work, and other medicines may affect the way docetaxel works.

Know the medicines you take. Keep a list of them to show your healthcare provider and pharmacist when you get a new medicine.

How will I receive Docetaxel injection?

- Docetaxel will be given to you as an intravenous (IV) injection into your vein, usually over 1 hour.
- Docetaxel is usually given every 3 weeks.
- Your healthcare provider will decide how long you will receive treatment with docetaxel.
- Your healthcare provider will check your blood cell counts and other blood tests during your treatment with docetaxel to check for side effects of docetaxel.
- Your healthcare provider may stop your treatment, change the timing of your treatment, or change the dose of your treatment if you have certain side effects while receiving docetaxel.

What are the possible side effects of Docetaxel injection?

Docetaxel may cause serious side effects including death.

- See " What is the most important information I should know about Docetaxel injection?"
- Neurologic problems.Neurologic symptoms are common in people who receive docetaxel but can be severe. Tell your healthcare provider right away if you have numbness, tingling, or burning in your hands or feet (peripheral neuropathy) or weakness of your legs, feet, arms, or hands (motor weakness).
- Vision problemsincluding blurred vision or loss of vision. Tell your healthcare provider right away if you have any vision changes.
- Docetaxel injection contains alcohol.The alcohol content in docetaxel may impair your ability to drive or use machinery right after receiving docetaxel. Consider whether you should drive, operate machinery or do other dangerous activities right after you receive docetaxel treatment.
- Tumor lysis syndrome (TLS).TLS is caused by the fast breakdown of cancer cells. TLS can cause kidney failure, the need for dialysis treatment, or heart problems, and may lead to death. Your healthcare provider will do blood tests to check for TLS when you first start treatment and during treatment with docetaxel. Tell your healthcare provider right away if you have any symptoms of TLS during treatment with docetaxel, including:

- nausea
- vomiting
- confusion
- shortness of breath

- irregular heartbeat
- dark or cloudy urine
- reduced amount of urine
- unusual tiredness
- muscle cramps

- You may experience side effects of this medicine that may impair your ability to drive, use tools, or operate machines. If this happens, do not drive or use any tools or machines before discussing with your healthcare provider.

The most common side effects of Docetaxel injection include:

- infections
- low white blood cells (help fight infections), low red blood cells (anemia) and low platelets (help blood to clot)
- allergic reactions (See " What is the most important information I should know about Docetaxel injection?")
- changes in your sense of taste
- shortness of breath
- constipation
- decreased appetite
- changes in your fingernails or toenails
- swelling of your hands, face or feet

- feeling weak or tired
- joint and muscle pain
- nausea and vomiting
- diarrhea
- mouth or lip sores
- hair loss: in some people, permanent hair loss has been reported
- redness of the eye, excess tearing
- skin reactions at the site of docetaxel administration such as increased skin pigmentation, redness, tenderness, swelling, warmth or dryness of the skin
- tissue damage if docetaxel leaks out of the vein into the tissues

Tell your healthcare provider if you have a fast or irregular heartbeat, severe shortness of breath, dizziness or fainting during your infusion. If any of these events occurs after your infusion, get medical help right away.

Docetaxel may affect fertility in males. Talk to your healthcare provider if this is a concern for you.

These are not all of the possible side effects of docetaxel. For more information, ask your healthcare provider or pharmacist.

Call your healthcare provider for medical advice about side effects. You may report side effects to FDA at 1-800-FDA-1088.

General information about the safe and effective use of Docetaxel injection.

Medicines are sometimes prescribed for purposes other than those listed in this Patient Information. You can ask your pharmacist or healthcare provider for information about docetaxel that is written for health professionals.

What are the ingredients in Docetaxel injection?

Active ingredient:docetaxel

Inactive ingredients:polysorbate 80 and dehydrated alcohol solution, with citric acid for pH adjustment

Winthrop U.S.,
a business of sanofi-aventis U.S. LLC
Bridgewater, NJ 08807
A SANOFI COMPANY
©2023 sanofi-aventis U.S. LLC

This Patient Information has been approved by the U.S. Food and Drug Administration.

Revised: January 2023

Every three-week injection of docetaxel for breast, non-small cell lung and stomach, and head and neck cancers

Take your oral corticosteroid medicine as your healthcare provider tells you.

Oral corticosteroid dosing:

Day 1Date:_________ Time: _______ AM _______ PM

Day 2Date:_________ Time: _______ AM _______ PM
(Docetaxel Treatment Day)

Day 3Date:_________ Time: _______ AM _______ PM

Every three-week injection of docetaxel for prostate cancer

Take your oral corticosteroid medicine as your healthcare provider tells you.

Oral corticosteroid dosing:

Date: ___________ Time: ___________

Date: ___________ Time: ___________
(Docetaxel Treatment Day)

Time: ___________

PRINCIPAL DISPLAY PANEL - 4 mL Vial Carton

Winthrop
A SANOFI COMPANY

NDC 0955-1021-04
Rx only

Docetaxel
Injection

80 mg/4 mL
(20 mg/mL)

READY TO ADD TO INFUSION SOLUTION
For Intravenous Infusion Only

One 4 mL single-dose vial.
Discard unused portion.

sanofi

PRINCIPAL DISPLAY PANEL - 1 mL Vial Carton

Winthrop
A SANOFI COMPANY

NDC 0955-1020-01
Rx only

Docetaxel
Injection

20 mg/mL

READY TO ADD TO INFUSION SOLUTION
For Intravenous Infusion Only

One 1 mL single-dose vial.
Discard unused portion.

sanofi

PRINCIPAL DISPLAY PANEL - 8 mL Vial Carton

Winthrop
A SANOFI COMPANY

NDC 0955-1022-08
Rx only

Docetaxel
Injection

160 mg/8 mL
(20 mg/mL)

READY TO ADD TO INFUSION SOLUTION
For Intravenous Infusion Only

One 8 mL single-dose vial.
Discard unused portion.

sanofi